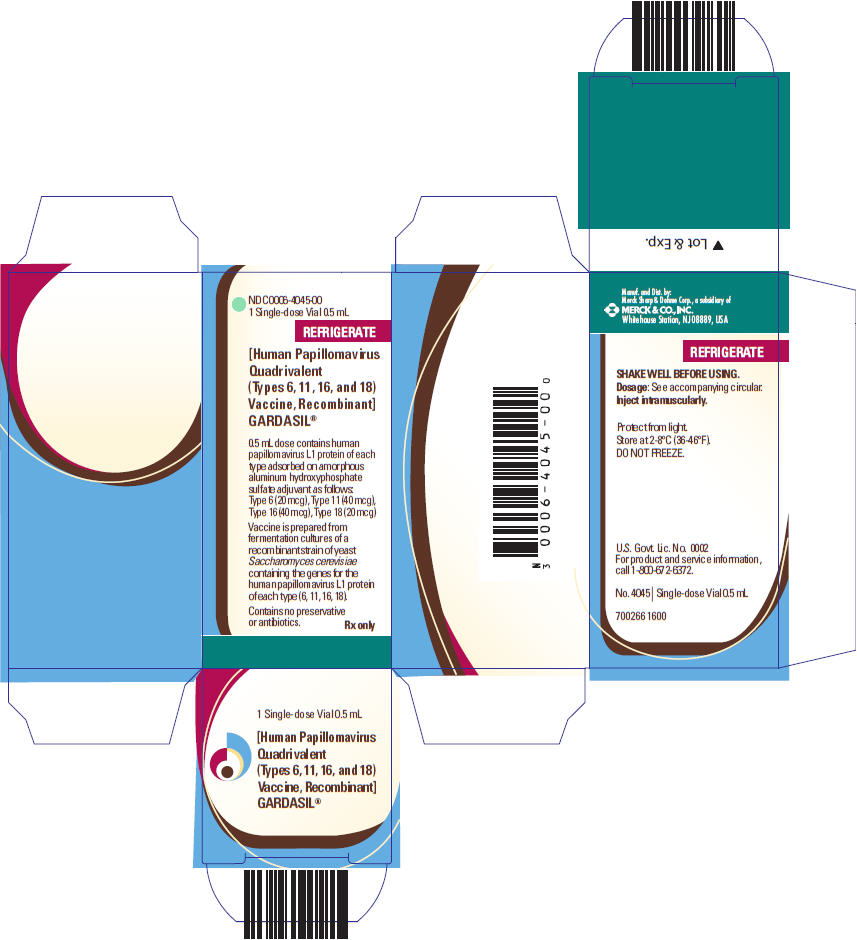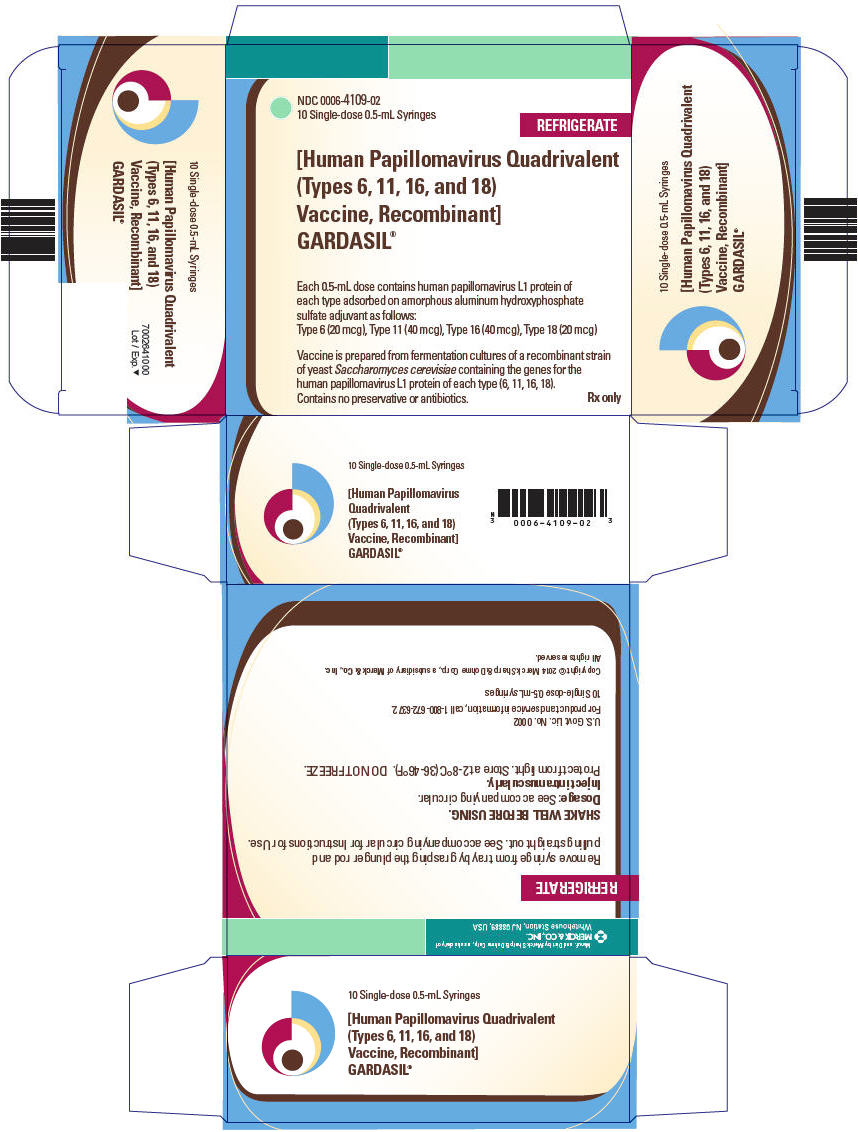 DRUG LABEL: GARDASIL
NDC: 0006-4045 | Form: INJECTION, SUSPENSION
Manufacturer: Merck Sharp & Dohme LLC
Category: other | Type: VACCINE LABEL
Date: 20250402

ACTIVE INGREDIENTS: HUMAN PAPILLOMAVIRUS TYPE 6 L1 CAPSID PROTEIN ANTIGEN 20 ug/0.5 mL; HUMAN PAPILLOMAVIRUS TYPE 11 L1 CAPSID PROTEIN ANTIGEN 40 ug/0.5 mL; HUMAN PAPILLOMAVIRUS TYPE 16 L1 CAPSID PROTEIN ANTIGEN 40 ug/0.5 mL; HUMAN PAPILLOMAVIRUS TYPE 18 L1 CAPSID PROTEIN ANTIGEN 20 ug/0.5 mL
INACTIVE INGREDIENTS: HISTIDINE 0.78 mg/0.5 mL; POLYSORBATE 80 50 ug/0.5 mL; SODIUM BORATE 35 ug/0.5 mL; SODIUM CHLORIDE 9.56 mg/0.5 mL; WATER

HIGHLIGHTS OF PRESCRIBING INFORMATION

These highlights do not include all the information needed to use GARDASIL safely and effectively. See full prescribing information for GARDASIL.
GARDASIL®
[Human Papillomavirus Quadrivalent (Types 6, 11, 16, and 18) Vaccine, Recombinant]
Suspension for intramuscular injection
Initial U.S. Approval: 2006

1 INDICATIONS AND USAGE

GARDASIL is a vaccine indicated in girls and women 9 through 26 years of age for the prevention of the following diseases caused by Human Papillomavirus (HPV) types included in the vaccine:

- Cervical, vulvar, vaginal, and anal cancer caused by HPV types 16 and 18. (1.1)
- Genital warts (condyloma acuminata) caused by HPV types 6 and 11. (1.1)

And the following precancerous or dysplastic lesions caused by HPV types 6, 11, 16, and 18:

- Cervical intraepithelial neoplasia (CIN) grade 2/3 and Cervical adenocarcinoma in situ (AIS). (1.1)
- Cervical intraepithelial neoplasia (CIN) grade 1. (1.1)
- Vulvar intraepithelial neoplasia (VIN) grade 2 and grade 3. (1.1)
- Vaginal intraepithelial neoplasia (VaIN) grade 2 and grade 3. (1.1)
- Anal intraepithelial neoplasia (AIN) grades 1, 2, and 3. (1.1)

GARDASIL is indicated in boys and men 9 through 26 years of age for the prevention of the following diseases caused by HPV types included in the vaccine:

- Anal cancer caused by HPV types 16 and 18. (1.2)
- Genital warts (condyloma acuminata) caused by HPV types 6 and 11. (1.2)

And the following precancerous or dysplastic lesions caused by HPV types 6, 11, 16, and 18:

- Anal intraepithelial neoplasia (AIN) grades 1, 2, and 3. (1.2)

Limitations of GARDASIL Use and Effectiveness:

- GARDASIL does not eliminate the necessity for women to continue to undergo recommended cervical cancer screening. (1.3, 17)
- Recipients of GARDASIL should not discontinue anal cancer screening if it has been recommended by a health care provider. (1.3, 17)
- GARDASIL has not been demonstrated to provide protection against disease from vaccine and non-vaccine HPV types to which a person has previously been exposed through sexual activity. (1.3, 14.4, 14.5)
- GARDASIL is not intended to be used for treatment of active external genital lesions; cervical, vulvar, vaginal, and anal cancers; CIN; VIN; VaIN, or AIN. (1.3)
- GARDASIL has not been demonstrated to protect against diseases due to HPV types not contained in the vaccine. (1.3, 14.4, 14.5)
- Not all vulvar, vaginal, and anal cancers are caused by HPV, and GARDASIL protects only against those vulvar, vaginal, and anal cancers caused by HPV 16 and 18. (1.3)
- GARDASIL does not protect against genital diseases not caused by HPV. (1.3)
- Vaccination with GARDASIL may not result in protection in all vaccine recipients. (1.3)
- GARDASIL has not been demonstrated to prevent HPV-related CIN 2/3 or worse in women older than 26 years of age. (14.7)

2 DOSAGE AND ADMINISTRATION

0.5-mL suspension for intramuscular injection at the following schedule: 0, 2 months, 6 months. (2.1)

3 DOSAGE FORMS AND STRENGTHS

- 0.5-mL suspension for injection as a single-dose vial and prefilled syringe. (3, 11)

4 CONTRAINDICATIONS

- Hypersensitivity, including severe allergic reactions to yeast (a vaccine component), or after a previous dose of GARDASIL. (4, 11)

5 WARNINGS AND PRECAUTIONS

- Because vaccinees may develop syncope, sometimes resulting in falling with injury, observation for 15 minutes after administration is recommended. Syncope, sometimes associated with tonic-clonic movements and other seizure-like activity, has been reported following vaccination with GARDASIL. When syncope is associated with tonic-clonic movements, the activity is usually transient and typically responds to restoring cerebral perfusion by maintaining a supine or Trendelenburg position. (5.1)

6 ADVERSE REACTIONS

The most common adverse reaction was headache. Common adverse reactions (frequency of at least 1.0% and greater than AAHS control or saline placebo) are fever, nausea, dizziness; and injection-site pain, swelling, erythema, pruritus, and bruising. (6.1)
To report SUSPECTED ADVERSE REACTIONS, contact Merck Sharp & Dohme LLC at 1-877-888-4231 or VAERS at 1-800-822-7967 or www.vaers.hhs.gov .

7 DRUG INTERACTIONS

GARDASIL may be administered concomitantly with RECOMBIVAX HB® (7.1) or with Menactra and Adacel. (7.2)

8 USE IN SPECIFIC POPULATIONS

Safety and effectiveness of GARDASIL have not been established in the following populations:

- Pregnant women. Women who receive GARDASIL during pregnancy are encouraged to contact Merck Sharp & Dohme LLC at 1-877-888-4231. (8.1)
- Children below the age of 9 years. (8.4)
- Immunocompromised individuals. Response to GARDASIL may be diminished. (8.6)

FULL PRESCRIBING INFORMATION

1 INDICATIONS AND USAGE

1.1 Girls and Women

GARDASIL® is a vaccine indicated in girls and women 9 through 26 years of age for the prevention of the following diseases caused by Human Papillomavirus (HPV) types included in the vaccine:

- Cervical, vulvar, vaginal, and anal cancer caused by HPV types 16 and 18
- Genital warts (condyloma acuminata) caused by HPV types 6 and 11

And the following precancerous or dysplastic lesions caused by HPV types 6, 11, 16, and 18:

- Cervical intraepithelial neoplasia (CIN) grade 2/3 and Cervical adenocarcinoma in situ (AIS)
- Cervical intraepithelial neoplasia (CIN) grade 1
- Vulvar intraepithelial neoplasia (VIN) grade 2 and grade 3
- Vaginal intraepithelial neoplasia (VaIN) grade 2 and grade 3
- Anal intraepithelial neoplasia (AIN) grades 1, 2, and 3

1.2 Boys and Men

GARDASIL is indicated in boys and men 9 through 26 years of age for the prevention of the following diseases caused by HPV types included in the vaccine:

- Anal cancer caused by HPV types 16 and 18
- Genital warts (condyloma acuminata) caused by HPV types 6 and 11

And the following precancerous or dysplastic lesions caused by HPV types 6, 11, 16, and 18:

- Anal intraepithelial neoplasia (AIN) grades 1, 2, and 3

1.3 Limitations of GARDASIL Use and Effectiveness

The health care provider should inform the patient, parent, or guardian that vaccination does not eliminate the necessity for women to continue to undergo recommended cervical cancer screening. Women who receive GARDASIL should continue to undergo cervical cancer screening per standard of care. [See Patient Counseling Information (17).]

Recipients of GARDASIL should not discontinue anal cancer screening if it has been recommended by a health care provider. [See Patient Counseling Information (17).]

GARDASIL has not been demonstrated to provide protection against disease from vaccine and non-vaccine HPV types to which a person has previously been exposed through sexual activity. [See Clinical Studies (14.4, 14.5).]

GARDASIL is not intended to be used for treatment of active external genital lesions; cervical, vulvar, vaginal, and anal cancers; CIN; VIN; VaIN; or AIN.

GARDASIL has not been demonstrated to protect against diseases due to HPV types not contained in the vaccine. [See Clinical Studies (14.4, 14.5).]

Not all vulvar, vaginal, and anal cancers are caused by HPV, and GARDASIL protects only against those vulvar, vaginal, and anal cancers caused by HPV 16 and 18.

GARDASIL does not protect against genital diseases not caused by HPV.

Vaccination with GARDASIL may not result in protection in all vaccine recipients.

GARDASIL has not been demonstrated to prevent HPV-related CIN 2/3 or worse in women older than 26 years of age. [See Clinical Studies (14.7).]

2 DOSAGE AND ADMINISTRATION

2.1 Dosage

GARDASIL should be administered intramuscularly as a 0.5-mL dose at the following schedule: 0, 2 months, 6 months. [See Clinical Studies (14.8).]

2.2 Method of Administration

For intramuscular use only.

Shake well before use. Thorough agitation immediately before administration is necessary to maintain suspension of the vaccine. GARDASIL should not be diluted or mixed with other vaccines. After thorough agitation, GARDASIL is a white, cloudy liquid. Parenteral drug products should be inspected visually for particulate matter and discoloration prior to administration. Do not use the product if particulates are present or if it appears discolored.

GARDASIL should be administered intramuscularly in the deltoid region of the upper arm or in the higher anterolateral area of the thigh.

Syncope has been reported following vaccination with GARDASIL and may result in falling with injury; observation for 15 minutes after administration is recommended. [See Warnings and Precautions (5.1).]

Single-Dose Vial Use

Withdraw the 0.5-mL dose of vaccine from the single-dose vial using a sterile needle and syringe and use promptly.

Prefilled Syringe Use

This package does not contain a needle. Shake well before use. Attach the needle by twisting in a clockwise direction until the needle fits securely on the syringe. Administer the entire dose as per standard protocol.

3 DOSAGE FORMS AND STRENGTHS

GARDASIL is a suspension for intramuscular administration available in 0.5-mL single dose vials and prefilled syringes. See Description (11) for the complete listing of ingredients.

4 CONTRAINDICATIONS

Hypersensitivity, including severe allergic reactions to yeast (a vaccine component), or after a previous dose of GARDASIL. [See Description (11).]

5 WARNINGS AND PRECAUTIONS

5.1 Syncope

Because vaccinees may develop syncope, sometimes resulting in falling with injury, observation for 15 minutes after administration is recommended. Syncope, sometimes associated with tonic-clonic movements and other seizure-like activity, has been reported following vaccination with GARDASIL. When syncope is associated with tonic-clonic movements, the activity is usually transient and typically responds to restoring cerebral perfusion by maintaining a supine or Trendelenburg position.

5.2 Managing Allergic Reactions

Appropriate medical treatment and supervision must be readily available in case of anaphylactic reactions following the administration of GARDASIL.

6 ADVERSE REACTIONS

Overall Summary of Adverse Reactions

Headache, fever, nausea, and dizziness; and local injection site reactions (pain, swelling, erythema, pruritus, and bruising) occurred after administration with GARDASIL.

Syncope, sometimes associated with tonic-clonic movements and other seizure-like activity, has been reported following vaccination with GARDASIL and may result in falling with injury; observation for 15 minutes after administration is recommended. [See Warnings and Precautions (5.1).]

Anaphylaxis has been reported following vaccination with GARDASIL.

6.1 Clinical Trials Experience

Because clinical trials are conducted under widely varying conditions, adverse reaction rates observed in the clinical trials of a vaccine cannot be directly compared to rates in the clinical trials of another vaccine and may not reflect the rates observed in practice.

Studies in Girls and Women (9 Through 45 Years of Age) and Boys and Men (9 Through 26 Years of Age)

In 7 clinical trials (5 Amorphous Aluminum Hydroxyphosphate Sulfate [AAHS]-controlled, 1 saline placebo-controlled, and 1 uncontrolled), 18,083 individuals were administered GARDASIL or AAHS control or saline placebo on the day of enrollment, and approximately 2 and 6 months thereafter, and safety was evaluated using vaccination report cards (VRC)-aided surveillance for 14 days after each injection of GARDASIL or AAHS control or saline placebo in these individuals. The individuals who were monitored using VRC-aided surveillance included 10,088 individuals 9 through 45 years of age at enrollment who received GARDASIL and 7,995 individuals who received AAHS control or saline placebo. Few individuals (0.2%) discontinued due to adverse reactions. The race distribution of the 9- through 26-year-old girls and women in the safety population was as follows: 62.3% White; 17.6% Hispanic (Black and White); 6.8% Asian; 6.7% Other; 6.4% Black; and 0.3% American Indian. The race distribution of the 24- through 45-year-old women in the safety population of Study 6 was as follows: 20.6% White; 43.2% Hispanic (Black and White); 0.2% Other; 4.8% Black; 31.2% Asian; and 0.1% American Indian. The race distribution of the 9- through 26-year-old boys and men in the safety population was as follows: 42.0% White; 19.7% Hispanic (Black and White); 11.0% Asian; 11.2% Other; 15.9% Black; and 0.1% American Indian.

Common Injection-Site Adverse Reactions in Girls and Women 9 Through 26 Years of Age

The injection site adverse reactions that were observed among recipients of GARDASIL at a frequency of at least 1.0% and also at a greater frequency than that observed among AAHS control or saline placebo recipients are shown in Table 1.

Table 1: Injection-Site Adverse Reactions in Girls and Women 9 Through 26 Years of Age [The injection-site adverse reactions that were observed among recipients of GARDASIL were at a frequency of at least 1.0% and also at a greater frequency than that observed among AAHS control or saline placebo recipients.]
Adverse Reaction (1 to 5 Days Postvaccination) | GARDASIL (N = 5088) % | AAHS Control [AAHS Control = Amorphous Aluminum Hydroxyphosphate Sulfate] (N = 3470) % | Saline Placebo (N = 320) %
Injection Site
Pain | 83.9 | 75.4 | 48.6
Swelling | 25.4 | 15.8 | 7.3
Erythema | 24.7 | 18.4 | 12.1
Pruritus | 3.2 | 2.8 | 0.6
Bruising | 2.8 | 3.2 | 1.6

Common Injection-Site Adverse Reactions in Boys and Men 9 Through 26 Years of Age

The injection site adverse reactions that were observed among recipients of GARDASIL at a frequency of at least 1.0% and also at a greater frequency than that observed among AAHS control or saline placebo recipients are shown in Table 2.

Table 2: Injection-Site Adverse Reactions in Boys and Men 9 Through 26 Years of Age [The injection-site adverse reactions that were observed among recipients of GARDASIL were at a frequency of at least 1.0% and also at a greater frequency than that observed among AAHS control or saline placebo recipients.]
Adverse Reaction (1 to 5 Days Postvaccination) | GARDASIL (N = 3093) % | AAHS Control [AAHS Control = Amorphous Aluminum Hydroxyphosphate Sulfate] (N = 2029) % | Saline Placebo (N = 274) %
Injection Site
Pain | 61.4 | 50.8 | 41.6
Erythema | 16.7 | 14.1 | 14.5
Swelling | 13.9 | 9.6 | 8.2
Hematoma | 1.0 | 0.3 | 3.3

Evaluation of Injection-Site Adverse Reactions by Dose in Girls and Women 9 Through 26 Years of Age

An analysis of injection-site adverse reactions in girls and women by dose is shown in Table 3. Of those girls and women who reported an injection-site reaction, 94.3% judged their injection-site adverse reaction to be mild or moderate in intensity.

Table 3: Postdose Evaluation of Injection-Site Adverse Reactions in Girls and Women 9 Through 26 Years of Age (1 to 5 Days Postvaccination)
 | GARDASIL (% occurrence) |  |  | AAHS Control [AAHS Control = Amorphous Aluminum Hydroxyphosphate Sulfate] (% occurrence) |  |  | Saline Placebo (% occurrence)
Adverse Reaction | Post-dose 1 N [N = Number of individuals with follow-up] = 5011 | Post-dose 2 N = 4924 | Post-dose 3 N = 4818 | Post-dose 1 N = 3410 | Post-dose 2 N = 3351 | Post-dose 3 N = 3295 | Post-dose 1 N = 315 | Post-dose 2 N = 301 | Post-dose 3 N = 300
Pain | 63.4 | 60.7 | 62.7 | 57.0 | 47.8 | 49.6 | 33.7 | 20.3 | 27.3
Mild/Moderate | 62.5 | 59.7 | 61.2 | 56.6 | 47.3 | 48.9 | 33.3 | 20.3 | 27.0
Severe | 0.9 | 1.0 | 1.5 | 0.4 | 0.5 | 0.6 | 0.3 | 0.0 | 0.3
Swelling [Intensity of swelling and erythema was measured by size (inches): Mild = 0 to ≤1; Moderate = >1 to ≤2; Severe = >2.] | 10.2 | 12.8 | 15.1 | 8.2 | 7.5 | 7.6 | 4.4 | 3.0 | 3.3
Mild/Moderate | 9.6 | 11.9 | 14.2 | 8.1 | 7.2 | 7.3 | 4.4 | 3.0 | 3.3
Severe | 0.6 | 0.8 | 0.9 | 0.2 | 0.2 | 0.2 | 0.0 | 0.0 | 0.0
Erythema | 9.2 | 12.1 | 14.7 | 9.8 | 8.4 | 8.9 | 7.3 | 5.3 | 5.7
Mild/Moderate | 9.0 | 11.7 | 14.3 | 9.5 | 8.4 | 8.8 | 7.3 | 5.3 | 5.7
Severe | 0.2 | 0.3 | 0.4 | 0.3 | 0.1 | 0.1 | 0.0 | 0.0 | 0.0

Evaluation of Injection-Site Adverse Reactions by Dose in Boys and Men 9 Through 26 Years of Age

An analysis of injection-site adverse reactions in boys and men by dose is shown in Table 4. Of those boys and men who reported an injection-site reaction, 96.4% judged their injection-site adverse reaction to be mild or moderate in intensity.

Table 4: Postdose Evaluation of Injection-Site Adverse Reactions in Boys and Men 9 Through 26 Years of Age (1 to 5 Days Postvaccination)
 | GARDASIL (% occurrence) |  |  | AAHS Control [AAHS Control = Amorphous Aluminum Hydroxyphosphate Sulfate] (% occurrence) |  |  | Saline Placebo (% occurrence)
Adverse Reaction | Post-dose 1 N [N = Number of individuals with follow-up] = 3003 | Post-dose 2 N = 2898 | Post-dose 3 N = 2826 | Post-dose 1 N = 1950 | Post-dose 2 N = 1854 | Post-dose 3 N = 1799 | Post-dose 1 N = 269 | Post-dose 2 N = 263 | Post-dose 3 N = 259
Pain | 44.7 | 36.9 | 34.4 | 38.4 | 28.2 | 25.8 | 27.5 | 20.5 | 16.2
Mild/Moderate | 44.5 | 36.4 | 34.1 | 37.9 | 28.2 | 25.5 | 27.5 | 20.2 | 16.2
Severe | 0.2 | 0.5 | 0.3 | 0.4 | 0.1 | 0.3 | 0.0 | 0.4 | 0.0
Swelling [Intensity of swelling and erythema was measured by size (inches): Mild = 0 to ≤1; Moderate = >1 to ≤2; Severe = >2.] | 5.6 | 6.6 | 7.7 | 5.6 | 4.5 | 4.1 | 4.8 | 1.5 | 3.5
Mild/Moderate | 5.3 | 6.2 | 7.1 | 5.4 | 4.5 | 4.0 | 4.8 | 1.5 | 3.1
Severe | 0.2 | 0.3 | 0.5 | 0.2 | 0.0 | 0.1 | 0.0 | 0.0 | 0.4
Erythema | 7.2 | 8.0 | 8.7 | 8.3 | 6.3 | 5.7 | 7.1 | 5.7 | 5.0
Mild/Moderate | 6.8 | 7.7 | 8.3 | 8.0 | 6.2 | 5.6 | 7.1 | 5.7 | 5.0
Severe | 0.3 | 0.2 | 0.3 | 0.2 | 0.1 | 0.1 | 0.0 | 0.0 | 0.0

Common Systemic Adverse Reactions in Girls and Women 9 Through 26 Years of Age

Headache was the most commonly reported systemic adverse reaction in both treatment groups (GARDASIL = 28.2% and AAHS control or saline placebo = 28.4%). Fever was the next most commonly reported systemic adverse reaction in both treatment groups (GARDASIL = 13.0% and AAHS control or saline placebo = 11.2%).

Adverse reactions that were observed among recipients of GARDASIL, at a frequency of greater than or equal to 1.0% where the incidence in the GARDASIL group was greater than or equal to the incidence in the AAHS control or saline placebo group, are shown in Table 5.

Table 5: Common Systemic Adverse Reactions in Girls and Women 9 Through 26 Years of Age (GARDASIL ≥Control) [The adverse reactions in this table are those that were observed among recipients of GARDASIL at a frequency of at least 1.0% and greater than or equal to those observed among AAHS control or saline placebo recipients.]
Adverse Reactions (1 to 15 Days Postvaccination) | GARDASIL (N = 5088) % | AAHS Control [AAHS Control = Amorphous Aluminum Hydroxyphosphate Sulfate] or Saline Placebo (N = 3790) %
Pyrexia | 13.0 | 11.2
Nausea | 6.7 | 6.5
Dizziness | 4.0 | 3.7
Diarrhea | 3.6 | 3.5
Vomiting | 2.4 | 1.9
Cough | 2.0 | 1.5
Toothache | 1.5 | 1.4
Upper respiratory tract infection | 1.5 | 1.5
Malaise | 1.4 | 1.2
Arthralgia | 1.2 | 0.9
Insomnia | 1.2 | 0.9
Nasal congestion | 1.1 | 0.9

Common Systemic Adverse Reactions in Boys and Men 9 Through 26 Years of Age

Headache was the most commonly reported systemic adverse reaction in both treatment groups (GARDASIL = 12.3% and AAHS control or saline placebo = 11.2%). Fever was the next most commonly reported systemic adverse reaction in both treatment groups (GARDASIL = 8.3% and AAHS control or saline placebo = 6.5%).

Adverse reactions that were observed among recipients of GARDASIL, at a frequency of greater than or equal to 1.0% where the incidence in the group that received GARDASIL was greater than or equal to the incidence in the AAHS control or saline placebo group, are shown in Table 6.

Table 6: Common Systemic Adverse Reactions in Boys and Men 9 Through 26 Years of Age (GARDASIL ≥Control) [The adverse reactions in this table are those that were observed among recipients of GARDASIL at a frequency of at least 1.0% and greater than or equal to those observed among AAHS control or saline placebo recipients.]
Adverse Reactions (1 to 15 Days Postvaccination) | GARDASIL (N = 3093) % | AAHS Control [AAHS Control = Amorphous Aluminum Hydroxyphosphate Sulfate] or Saline Placebo (N = 2303) %
Headache | 12.3 | 11.2
Pyrexia | 8.3 | 6.5
Oropharyngeal pain | 2.8 | 2.1
Diarrhea | 2.7 | 2.2
Nasopharyngitis | 2.6 | 2.6
Nausea | 2.0 | 1.0
Upper respiratory tract infection | 1.5 | 1.0
Abdominal pain upper | 1.4 | 1.4
Myalgia | 1.3 | 0.7
Dizziness | 1.2 | 0.9
Vomiting | 1.0 | 0.8

Evaluation of Fever by Dose in Girls and Women 9 Through 26 Years of Age

An analysis of fever in girls and women by dose is shown in Table 7.

Table 7: Postdose Evaluation of Fever in Girls and Women 9 Through 26 Years of Age (1 to 5 Days Postvaccination)
 | GARDASIL (% occurrence) |  |  | AAHS Control [AAHS Control = Amorphous Aluminum Hydroxyphosphate Sulfate] or Saline Placebo (% occurrence)
Temperature (°F) | Postdose 1 N [N = Number of individuals with follow-up] = 4945 | Postdose 2 N = 4804 | Postdose 3 N = 4671 | Postdose 1 N = 3681 | Postdose 2 N = 3564 | Postdose 3 N = 3467
≥100 to <102 | 3.7 | 4.1 | 4.4 | 3.1 | 3.8 | 3.6
≥102 | 0.3 | 0.5 | 0.5 | 0.2 | 0.4 | 0.5

Evaluation of Fever by Dose in Boys and Men 9 Through 26 Years of Age

An analysis of fever in boys and men by dose is shown in Table 8.

Table 8: Postdose Evaluation of Fever in Boys and Men 9 Through 26 Years of Age (1 to 5 Days Postvaccination)
 | GARDASIL (% occurrence) |  |  | AAHS Control [AAHS Control = Amorphous Aluminum Hydroxyphosphate Sulfate] or Saline Placebo (% occurrence)
Temperature (°F) | Postdose 1 N [N = Number of individuals with follow-up] = 2972 | Postdose 2 N = 2849 | Postdose 3 N = 2792 | Postdose 1 N = 2194 | Postdose 2 N = 2079 | Postdose 3 N = 2046
≥100 to <102 | 2.4 | 2.5 | 2.3 | 2.1 | 2.2 | 1.6
≥102 | 0.6 | 0.5 | 0.5 | 0.5 | 0.3 | 0.3

Serious Adverse Reactions in the Entire Study Population

Across the clinical studies, 258 individuals (GARDASIL N = 128 or 0.8%; placebo N = 130 or 1.0%) out of 29,323 (GARDASIL N = 15,706; AAHS control N = 13,023; or saline placebo N = 594) individuals (9- through 45-year-old girls and women; and 9- through 26-year-old boys and men) reported a serious systemic adverse reaction.

Of the entire study population (29,323 individuals), 0.04% of the reported serious systemic adverse reactions were judged to be vaccine related by the study investigator. The most frequently (frequency of 4 cases or greater with either GARDASIL, AAHS control, saline placebo, or the total of all three) reported serious systemic adverse reactions, regardless of causality, were:

Headache [0.02% GARDASIL (3 cases) vs. 0.02% AAHS control (2 cases)],
Gastroenteritis [0.02% GARDASIL (3 cases) vs. 0.02% AAHS control (2 cases)],
Appendicitis [0.03% GARDASIL (5 cases) vs. 0.01% AAHS control (1 case)],
Pelvic inflammatory disease [0.02% GARDASIL (3 cases) vs. 0.03% AAHS control (4 cases)],
Urinary tract infection [0.01% GARDASIL (2 cases) vs. 0.02% AAHS control (2 cases)],
Pneumonia [0.01% GARDASIL (2 cases) vs. 0.02% AAHS control (2 cases)],
Pyelonephritis [0.01% GARDASIL (2 cases) vs. 0.02% AAHS control (3 cases)],
Pulmonary embolism [0.01% GARDASIL (2 cases) vs. 0.02% AAHS control (2 cases)].

One case (0.006% GARDASIL; 0.0% AAHS control or saline placebo) of bronchospasm; and 2 cases (0.01% GARDASIL; 0.0% AAHS control or saline placebo) of asthma were reported as serious systemic adverse reactions that occurred following any vaccination visit.

In addition, there was 1 individual in the clinical trials, in the group that received GARDASIL, who reported two injection-site serious adverse reactions (injection-site pain and injection-site joint movement impairment).

Deaths in the Entire Study Population

Across the clinical studies, 40 deaths (GARDASIL N = 21 or 0.1%; placebo N = 19 or 0.1%) were reported in 29,323 (GARDASIL N = 15,706; AAHS control N = 13,023, saline placebo N = 594) individuals (9- through 45-year-old girls and women; and 9- through 26-year-old boys and men). The events reported were consistent with events expected in healthy adolescent and adult populations. The most common cause of death was motor vehicle accident (5 individuals who received GARDASIL and 4 individuals who received AAHS control), followed by drug overdose/suicide (2 individuals who received GARDASIL and 6 individuals who received AAHS control), gunshot wound (1 individual who received GARDASIL and 3 individuals who received AAHS control), and pulmonary embolus/deep vein thrombosis (1 individual who received GARDASIL and 1 individual who received AAHS control). In addition, there were 2 cases of sepsis, 1 case of pancreatic cancer, 1 case of arrhythmia, 1 case of pulmonary tuberculosis, 1 case of hyperthyroidism, 1 case of post-operative pulmonary embolism and acute renal failure, 1 case of traumatic brain injury/cardiac arrest, 1 case of systemic lupus erythematosus, 1 case of cerebrovascular accident, 1 case of breast cancer, and 1 case of nasopharyngeal cancer in the group that received GARDASIL; 1 case of asphyxia, 1 case of acute lymphocytic leukemia, 1 case of chemical poisoning, and 1 case of myocardial ischemia in the AAHS control group; and 1 case of medulloblastoma in the saline placebo group.

Systemic Autoimmune Disorders in Girls and Women 9 Through 26 Years of Age

In the clinical studies, 9- through 26-year-old girls and women were evaluated for new medical conditions that occurred over the course of follow-up. New medical conditions potentially indicative of a systemic autoimmune disorder seen in the group that received GARDASIL or AAHS control or saline placebo are shown in Table 9. This population includes all girls and women who received at least one dose of GARDASIL or AAHS control or saline placebo, and had safety data available.

Table 9: Summary of Girls and Women 9 Through 26 Years of Age Who Reported an Incident Condition Potentially Indicative of a Systemic Autoimmune Disorder After Enrollment in Clinical Trials of GARDASIL, Regardless of Causality
Conditions | GARDASIL (N = 10,706) | AAHS Control [AAHS Control = Amorphous Aluminum Hydroxyphosphate Sulfate] or Saline Placebo (N = 9412)
Conditions | n (%) | n (%)
Arthralgia/Arthritis/Arthropathy [Arthralgia/Arthritis/Arthropathy includes the following terms: Arthralgia, Arthritis, Arthritis reactive, and Arthropathy] | 120 (1.1) | 98 (1.0)
Autoimmune Thyroiditis | 4 (0.0) | 1 (0.0)
Celiac Disease | 10 (0.1) | 6 (0.1)
Diabetes Mellitus Insulin-dependent | 2 (0.0) | 2 (0.0)
Erythema Nodosum | 2 (0.0) | 4 (0.0)
Hyperthyroidism [Hyperthyroidism includes the following terms: Basedow's disease, Goiter, Toxic nodular goiter, and Hyperthyroidism] | 27 (0.3) | 21 (0.2)
Hypothyroidism [Hypothyroidism includes the following terms: Hypothyroidism and thyroiditis] | 35 (0.3) | 38 (0.4)
Inflammatory Bowel Disease [Inflammatory bowel disease includes the following terms: Colitis ulcerative, Crohn's disease, and Inflammatory bowel disease] | 7 (0.1) | 10 (0.1)
Multiple Sclerosis | 2 (0.0) | 4 (0.0)
Nephritis [Nephritis includes the following terms: Nephritis, Glomerulonephritis minimal lesion, Glomerulonephritis proliferative] | 2 (0.0) | 5 (0.1)
Optic Neuritis | 2 (0.0) | 0 (0.0)
Pigmentation Disorder [Pigmentation disorder includes the following terms: Pigmentation disorder, Skin depigmentation, and Vitiligo] | 4 (0.0) | 3 (0.0)
Psoriasis [Psoriasis includes the following terms: Psoriasis, Pustular psoriasis, and Psoriatic arthropathy] | 13 (0.1) | 15 (0.2)
Raynaud's Phenomenon | 3 (0.0) | 4 (0.0)
Rheumatoid Arthritis [Rheumatoid arthritis includes juvenile rheumatoid arthritis. One woman counted in the rheumatoid arthritis group reported rheumatoid arthritis as an adverse experience at Day 130.] | 6 (0.1) | 2 (0.0)
Scleroderma/Morphea | 2 (0.0) | 1 (0.0)
Stevens-Johnson Syndrome | 1 (0.0) | 0 (0.0)
Systemic Lupus Erythematosus | 1 (0.0) | 3 (0.0)
Uveitis | 3 (0.0) | 1 (0.0)
All Conditions | 245 (2.3) | 218 (2.3)
N = Number of individuals enrolled
n = Number of individuals with specific new Medical Conditions
NOTE: Although an individual may have had two or more new Medical Conditions, the individual is counted only once within a category. The same individual may appear in different categories.

Systemic Autoimmune Disorders in Boys and Men 9 Through 26 Years of Age

In the clinical studies, 9- through 26-year-old boys and men were evaluated for new medical conditions that occurred over the course of follow-up. New medical conditions potentially indicative of a systemic autoimmune disorder seen in the group that received GARDASIL or AAHS control or saline placebo are shown in Table 10. This population includes all boys and men who received at least one dose of GARDASIL or AAHS control or saline placebo, and had safety data available.

Table 10: Summary of Boys and Men 9 Through 26 Years of Age Who Reported an Incident Condition Potentially Indicative of a Systemic Autoimmune Disorder After Enrollment in Clinical Trials of GARDASIL, Regardless of Causality
Conditions | GARDASIL (N = 3093) | AAHS Control [AAHS Control = Amorphous Aluminum Hydroxyphosphate Sulfate] or Saline Placebo (N = 2303)
Conditions | n (%) | n (%)
Alopecia Areata | 2 (0.1) | 0 (0.0)
Ankylosing Spondylitis | 1 (0.0) | 2 (0.1)
Arthralgia/Arthritis/Reactive Arthritis | 30 (1.0) | 17 (0.7)
Autoimmune Thrombocytopenia | 1 (0.0) | 0 (0.0)
Diabetes Mellitus Type 1 | 3 (0.1) | 2 (0.1)
Hyperthyroidism | 0 (0.0) | 1 (0.0)
Hypothyroidism [Hypothyroidism includes the following terms: Hypothyroidism and Autoimmune thyroiditis] | 3 (0.1) | 0 (0.0)
Inflammatory Bowel Disease [Inflammatory bowel disease includes the following terms: Colitis ulcerative and Crohn's disease] | 1 (0.0) | 2 (0.1)
Myocarditis | 1 (0.0) | 1 (0.0)
Proteinuria | 1 (0.0) | 0 (0.0)
Psoriasis | 0 (0.0) | 4 (0.2)
Skin Depigmentation | 1 (0.0) | 0 (0.0)
Vitiligo | 2 (0.1) | 5 (0.2)
All Conditions | 46 (1.5) | 34 (1.5)
N = Number of individuals who received at least one dose of either vaccine or placebo
n = Number of individuals with specific new Medical Conditions
NOTE: Although an individual may have had two or more new Medical Conditions, the individual is counted only once within a category. The same individual may appear in different categories.

Safety in Concomitant Use with RECOMBIVAX HB® [hepatitis B vaccine (recombinant)] in Girls and Women 16 Through 23 Years of Age

The safety of GARDASIL when administered concomitantly with RECOMBIVAX HB® [hepatitis B vaccine (recombinant)] was evaluated in an AAHS-controlled study of 1871 girls and women with a mean age of 20.4 years [see Clinical Studies (14.10)]. The race distribution of the study individuals was as follows: 61.6% White; 23.8% Other; 11.9% Black; 1.6% Hispanic (Black and White); 0.8% Asian; and 0.3% American Indian. The rates of systemic and injection-site adverse reactions were similar among girls and women who received concomitant vaccination as compared with those who received GARDASIL or RECOMBIVAX HB [hepatitis B vaccine (recombinant)].

Safety in Concomitant Use with Menactra [Meningococcal (Groups A, C, Y and W-135) Polysaccharide Diphtheria Toxoid Conjugate Vaccine] and Adacel [Tetanus Toxoid, Reduced Diphtheria Toxoid and Acellular Pertussis Vaccine Adsorbed (Tdap)]

The safety of GARDASIL when administered concomitantly with Menactra [Meningococcal (Groups A, C, Y and W-135) Polysaccharide Diphtheria Toxoid Conjugate Vaccine] and Adacel [Tetanus Toxoid, Reduced Diphtheria Toxoid and Acellular Pertussis Vaccine Adsorbed (Tdap)] was evaluated in a randomized study of 1040 boys and girls with a mean age of 12.6 years [see Clinical Studies (14.11)]. The race distribution of the study subjects was as follows: 77.7% White; 1.4% Multi-racial; 12.3% Black; 6.8% Hispanic (Black and White); 1.2% Asian; 0.4% American Indian, and 0.2% Indian.

There was an increase in injection-site swelling reported at the injection site for GARDASIL (concomitant = 10.9%, non-concomitant = 6.9%) when GARDASIL was administered concomitantly with Menactra and Adacel as compared to non-concomitant (separated by 1 month) vaccination. The majority of injection-site swelling adverse experiences were reported as being mild to moderate in intensity.

Safety in Women 27 Through 45 Years of Age

The adverse reaction profile in women 27 through 45 years of age was comparable to the profile seen in girls and women 9 through 26 years of age.

6.2 Postmarketing Experience

The following adverse events have been spontaneously reported during post-approval use of GARDASIL. Because these events were reported voluntarily from a population of uncertain size, it is not possible to reliably estimate their frequency or to establish a causal relationship to vaccine exposure.

Blood and lymphatic system disorders: Autoimmune hemolytic anemia, idiopathic thrombocytopenic purpura, lymphadenopathy.

Respiratory, thoracic and mediastinal disorders: Pulmonary embolus.

Gastrointestinal disorders: Nausea, pancreatitis, vomiting.

General disorders and administration site conditions: Asthenia, chills, death, fatigue, malaise, injection-site nodule.

Immune system disorders: Autoimmune diseases, hypersensitivity reactions including anaphylactic/anaphylactoid reactions, bronchospasm, and urticaria.

Musculoskeletal and connective tissue disorders: Arthralgia, myalgia.

Nervous system disorders: Acute disseminated encephalomyelitis, dizziness, Guillain-Barré syndrome, headache, motor neuron disease, paralysis, seizures, syncope (including syncope associated with tonic-clonic movements and other seizure-like activity) sometimes resulting in falling with injury, transverse myelitis.

Infections and infestations: Cellulitis.

Vascular disorders: Deep venous thrombosis.

7 DRUG INTERACTIONS

7.1 Use with RECOMBIVAX HB

Results from clinical studies indicate that GARDASIL may be administered concomitantly (at a separate injection site) with RECOMBIVAX HB [hepatitis B vaccine (recombinant)] [see Clinical Studies (14.10)].

7.2 Use with Menactra and Adacel

Results from clinical studies indicate that GARDASIL may be administered concomitantly (at a separate injection site) with Menactra [Meningococcal (Groups A, C, Y and W-135) Polysaccharide Diphtheria Toxoid Conjugate Vaccine] and Adacel [Tetanus Toxoid, Reduced Diphtheria Toxoid and Acellular Pertussis Vaccine Adsorbed (Tdap)] [see Clinical Studies (14.11)].

7.3 Use with Hormonal Contraceptives

In clinical studies of 16- through 26-year-old women, 13,912 (GARDASIL N = 6952; AAHS control or saline placebo N = 6960) who had post-Month 7 follow-up used hormonal contraceptives for a total of 33,859 person-years (65.8% of the total follow-up time in the studies).

In one clinical study of 24- through 45-year-old women, 1357 (GARDASIL N = 690; AAHS control N = 667) who had post-Month 7 follow-up used hormonal contraceptives for a total of 3400 person-years (31.5% of the total follow-up time in the study). Use of hormonal contraceptives or lack of use of hormonal contraceptives among study participants did not impair the immune response in the per protocol immunogenicity (PPI) population.

7.4 Use with Systemic Immunosuppressive Medications

Immunosuppressive therapies, including irradiation, antimetabolites, alkylating agents, cytotoxic drugs, and corticosteroids (used in greater than physiologic doses), may reduce the immune responses to vaccines [see Use in Specific Populations (8.6)].

8 USE IN SPECIFIC POPULATIONS

8.1 Pregnancy

TERATOGENIC EFFECTS

Pregnancy Category B

Reproduction studies have been performed in female rats at doses equivalent to the recommended human dose and have revealed no evidence of impaired female fertility or harm to the fetus due to GARDASIL. There are, however, no adequate and well-controlled studies in pregnant women. Because animal reproduction studies are not always predictive of human responses, GARDASIL should be used during pregnancy only if clearly needed.

An evaluation of the effect of GARDASIL on embryo-fetal, pre- and postweaning development was conducted using rats. One group of rats was administered GARDASIL twice prior to gestation, during the period of organogenesis (gestation Day 6) and on lactation Day 7. A second group of pregnant rats was administered GARDASIL during the period of organogenesis (gestation Day 6) and on lactation Day 7 only. GARDASIL was administered at 0.5 mL/rat/occasion (120 mcg total protein which is equivalent to the recommended human dose) by intramuscular injection. No adverse effects on mating, fertility, pregnancy, parturition, lactation, embryo-fetal or pre- and postweaning development were observed. There were no vaccine-related fetal malformations or other evidence of teratogenesis noted in this study. In addition, there were no treatment-related effects on developmental signs, behavior, reproductive performance, or fertility of the offspring.

Clinical Studies in Humans

In clinical studies, women underwent urine pregnancy testing prior to administration of each dose of GARDASIL. Women who were found to be pregnant before completion of a 3-dose regimen of GARDASIL were instructed to defer completion of their vaccination regimen until resolution of the pregnancy.

GARDASIL is not indicated for women 27 years of age or older. However, safety data in women 16 through 45 years of age was collected, and 3819 women (GARDASIL N = 1894 vs. AAHS control or saline placebo N = 1925) reported at least 1 pregnancy each.

The overall proportions of pregnancies that resulted in an adverse outcome, defined as the combined numbers of spontaneous abortion, late fetal death, and congenital anomaly cases out of the total number of pregnancy outcomes for which an outcome was known (and excluding elective terminations), were 22.6% (446/1973) in women who received GARDASIL and 23.1% (460/1994) in women who received AAHS control or saline placebo.

Overall, 55 and 65 women in the group that received GARDASIL or AAHS control or saline placebo, respectively (2.9% and 3.4% of all women who reported a pregnancy in the respective vaccination groups), experienced a serious adverse reaction during pregnancy. The most common events reported were conditions that can result in Caesarean section (e.g., failure of labor, malpresentation, cephalopelvic disproportion), premature onset of labor (e.g., threatened abortions, premature rupture of membranes), and pregnancy-related medical problems (e.g., pre-eclampsia, hyperemesis). The proportions of pregnant women who experienced such events were comparable between the groups receiving GARDASIL and AAHS control or saline placebo.

There were 45 cases of congenital anomaly in pregnancies that occurred in women who received GARDASIL and 34 cases of congenital anomaly in pregnancies that occurred in women who received AAHS control or saline placebo.

Further sub-analyses were conducted to evaluate pregnancies with estimated onset within 30 days or more than 30 days from administration of a dose of GARDASIL or AAHS control or saline placebo. For pregnancies with estimated onset within 30 days of vaccination, 5 cases of congenital anomaly were observed in the group that received GARDASIL compared to 1 case of congenital anomaly in the group that received AAHS control or saline placebo. The congenital anomalies seen in pregnancies with estimated onset within 30 days of vaccination included pyloric stenosis, congenital megacolon, congenital hydronephrosis, hip dysplasia, and club foot. Conversely, in pregnancies with onset more than 30 days following vaccination, 40 cases of congenital anomaly were observed in the group that received GARDASIL compared with 33 cases of congenital anomaly in the group that received AAHS control or saline placebo.

Women who receive GARDASIL during pregnancy are encouraged to contact Merck Sharp & Dohme LLC at 1-877-888-4231 or VAERS at 1-800-822-7967 or www.vaers.hhs.gov .

8.3 Nursing Mothers

Women 16 Through 45 Years of Age

It is not known whether GARDASIL is excreted in human milk. Because many drugs are excreted in human milk, caution should be exercised when GARDASIL is administered to a nursing woman.

GARDASIL or AAHS control were given to a total of 1133 women (vaccine N = 582, AAHS control N = 551) during the relevant Phase 3 clinical studies.

Overall, 27 and 13 infants of women who received GARDASIL or AAHS control, respectively (representing 4.6% and 2.4% of the total number of women who were breast-feeding during the period in which they received GARDASIL or AAHS control, respectively), experienced a serious adverse reaction.

In a post-hoc analysis of clinical studies, a higher number of breast-feeding infants (n = 7) whose mothers received GARDASIL had acute respiratory illnesses within 30 days post vaccination of the mother as compared to infants (n = 2) whose mothers received AAHS control.

8.4 Pediatric Use

Safety and effectiveness have not been established in pediatric patients below 9 years of age.

8.5 Geriatric Use

The safety and effectiveness of GARDASIL have not been evaluated in a geriatric population, defined as individuals aged 65 years and over.

8.6 Immunocompromised Individuals

The immunologic response to GARDASIL may be diminished in immunocompromised individuals [see Drug Interactions (7.4)].

10 OVERDOSAGE

There have been reports of administration of higher than recommended doses of GARDASIL.

In general, the adverse event profile reported with overdose was comparable to recommended single doses of GARDASIL.

11 DESCRIPTION

GARDASIL, Human Papillomavirus Quadrivalent (Types 6, 11, 16, and 18) Vaccine, Recombinant, is a non-infectious recombinant quadrivalent vaccine prepared from the purified virus-like particles (VLPs) of the major capsid (L1) protein of HPV Types 6, 11, 16, and 18. The L1 proteins are produced by separate fermentations in recombinant Saccharomyces cerevisiae and self-assembled into VLPs. The fermentation process involves growth of S. cerevisiae on chemically-defined fermentation media which include vitamins, amino acids, mineral salts, and carbohydrates. The VLPs are released from the yeast cells by cell disruption and purified by a series of chemical and physical methods. The purified VLPs are adsorbed on preformed aluminum-containing adjuvant (Amorphous Aluminum Hydroxyphosphate Sulfate). The quadrivalent HPV VLP vaccine is a sterile liquid suspension that is prepared by combining the adsorbed VLPs of each HPV type and additional amounts of the aluminum-containing adjuvant and the final purification buffer.

GARDASIL is a sterile suspension for intramuscular administration. Each 0.5-mL dose contains approximately 20 mcg of HPV 6 L1 protein, 40 mcg of HPV 11 L1 protein, 40 mcg of HPV 16 L1 protein, and 20 mcg of HPV 18 L1 protein.

Each 0.5-mL dose of the vaccine contains approximately 225 mcg of aluminum (as Amorphous Aluminum Hydroxyphosphate Sulfate adjuvant), 9.56 mg of sodium chloride, 0.78 mg of L-histidine, 50 mcg of polysorbate 80, 35 mcg of sodium borate, <7 mcg yeast protein/dose, and water for injection. The product does not contain a preservative or antibiotics.

After thorough agitation, GARDASIL is a white, cloudy liquid.

12 CLINICAL PHARMACOLOGY

12.1 Mechanism of Action

HPV only infects human beings. Animal studies with analogous animal papillomaviruses suggest that the efficacy of L1 VLP vaccines may involve the development of humoral immune responses. Human beings develop a humoral immune response to the vaccine, although the exact mechanism of protection is unknown.

13 NONCLINICAL TOXICOLOGY

13.1 Carcinogenesis, Mutagenesis, Impairment of Fertility

GARDASIL has not been evaluated for the potential to cause carcinogenicity or genotoxicity.

GARDASIL administered to female rats at a dose of 120 mcg total protein, which is equivalent to the recommended human dose, had no effects on mating performance, fertility, or embryonic/fetal survival.

The effect of GARDASIL on male fertility has been studied in male rats at an intramuscular dose of 0.5 mL/rat/occasion (120 mcg total protein which is equivalent to the recommended human dose). One group of male rats was administered GARDASIL once, 3 days prior to cohabitation, and a second group of male rats was administered GARDASIL three times, at 6 weeks, 3 weeks, and 3 days prior to cohabitation. There were no treatment-related effects on reproductive performance including fertility, sperm count, and sperm motility. There were no treatment-related gross or histomorphologic and weight changes on the testes.

14 CLINICAL STUDIES

CIN 2/3 and AIS are the immediate and necessary precursors of squamous cell carcinoma and adenocarcinoma of the cervix, respectively. Their detection and removal has been shown to prevent cancer; thus, they serve as surrogate markers for prevention of cervical cancer. In the clinical studies in girls and women aged 16 through 26 years, cases of CIN 2/3 and AIS were the efficacy endpoints to assess prevention of cervical cancer. In addition, cases of VIN 2/3 and VaIN 2/3 were the efficacy endpoints to assess prevention of HPV-related vulvar and vaginal cancers, and observations of external genital lesions were the efficacy endpoints for the prevention of genital warts.

In clinical studies in boys and men aged 16 through 26 years, efficacy was evaluated using the following endpoints: external genital warts and penile/perineal/perianal intraepithelial neoplasia (PIN) grades 1/2/3 or penile/perineal/perianal cancer. In addition, cases of AIN grades 1/2/3 and anal cancer made up the composite efficacy endpoint used to assess prevention of HPV-related anal cancer.

Anal HPV infection, AIN, and anal cancer were not endpoints in the studies conducted in women. The similarity of HPV-related anal disease in men and women supports bridging the indication of prevention of AIN and anal cancer to women.

Efficacy was assessed in 6 AAHS-controlled, double-blind, randomized Phase 2 and 3 clinical studies. The first Phase 2 study evaluated the HPV 16 component of GARDASIL (Study 1, N = 2391 16- through 26-year-old girls and women) and the second evaluated all components of GARDASIL (Study 2, N = 551 16- through 26-year-old girls and women). Two Phase 3 studies evaluated GARDASIL in 5442 (Study 3) and 12,157 (Study 4) 16- through 26-year-old girls and women. A third Phase 3 study, Study 5, evaluated GARDASIL in 4055 16- through 26-year-old boys and men, including a subset of 598 (GARDASIL = 299; placebo = 299) men who self-identified as having sex with men (MSM population). A fourth Phase 3 study, Study 6, evaluated GARDASIL in 3817 24- through 45-year-old women. Together, these six studies evaluated 28,413 individuals (20,541 girls and women 16 through 26 years of age at enrollment with a mean age of 20.0 years, 4055 boys and men 16 through 26 years of age at enrollment with a mean age of 20.5 years, and 3817 women 24 through 45 years of age at enrollment with a mean age of 34.3 years). The race distribution of the 16- through 26-year-old girls and women in the clinical trials was as follows: 70.4% White; 12.2% Hispanic (Black and White); 8.8% Other; 4.6% Black; 3.8% Asian; and 0.2% American Indian. The race distribution of the 16- through 26-year-old boys and men in the clinical trials was as follows: 35.2% White; 20.5% Hispanic (Black and White); 14.4% Other; 19.8% Black; 10.0% Asian; and 0.1% American Indian. The race distribution of the 24- through 45-year-old women in the clinical trials was as follows: 20.6% White; 43.2% Hispanic (Black and White); 0.2% Other; 4.8% Black; 31.2% Asian; and 0.1% American Indian.

The median duration of follow-up was 4.0, 3.0, 3.0, 3.0, 2.3, and 4.0 years for Study 1, Study 2, Study 3, Study 4, Study 5, and Study 6, respectively. Individuals received vaccine or AAHS control on the day of enrollment and 2 and 6 months thereafter. Efficacy was analyzed for each study individually and for all studies in girls and women combined according to a prospective clinical plan.

Overall, 73% of 16- through 26-year-old girls and women, 67% of 24- through 45-year-old women, and 83% of 16- through 26-year-old boys and men were naïve (i.e., PCR [Polymerase Chain Reaction] negative and seronegative for all 4 vaccine HPV types) to all 4 vaccine HPV types at enrollment.

A total of 27% of 16- through 26-year-old girls and women, 33% of 24- through 45-year-old women, and 17% of 16- through 26-year-old boys and men had evidence of prior exposure to or ongoing infection with at least 1 of the 4 vaccine HPV types. Among these individuals, 74% of 16- through 26-year-old girls and women, 71% of 24- through 45-year-old women, and 78% of 16- through 26-year-old boys and men had evidence of prior exposure to or ongoing infection with only 1 of the 4 vaccine HPV types and were naïve (PCR negative and seronegative) to the remaining 3 types.

In 24- through 45-year-old individuals, 0.4% had been exposed to all 4 vaccine HPV types.

In individuals who were naïve (PCR negative and seronegative) to all 4 vaccine HPV types, CIN, genital warts, VIN, VaIN, PIN, and persistent infection caused by any of the 4 vaccine HPV types were counted as endpoints.

Among individuals who were positive (PCR positive and/or seropositive) for a vaccine HPV type at Day 1, endpoints related to that type were not included in the analyses of prophylactic efficacy. Endpoints related to the remaining types for which the individual was naïve (PCR negative and seronegative) were counted.

For example, in individuals who were HPV 18 positive (PCR positive and/or seropositive) at Day 1, lesions caused by HPV 18 were not counted in the prophylactic efficacy evaluations. Lesions caused by HPV 6, 11, and 16 were included in the prophylactic efficacy evaluations. The same approach was used for the other types.

14.1 Prophylactic Efficacy – HPV Types 6, 11, 16, and 18 in Girls and Women 16 through 26 Years of Age

GARDASIL was administered without prescreening for presence of HPV infection and the efficacy trials allowed enrollment of girls and women regardless of baseline HPV status (i.e., PCR status or serostatus). Girls and women with current or prior HPV infection with an HPV type contained in the vaccine were not eligible for prophylactic efficacy evaluations for that type.

The primary analyses of efficacy with respect to HPV types 6, 11, 16, and 18 were conducted in the per-protocol efficacy (PPE) population, consisting of girls and women who received all 3 vaccinations within 1 year of enrollment, did not have major deviations from the study protocol, and were naïve (PCR negative in cervicovaginal specimens and seronegative) to the relevant HPV type(s) (Types 6, 11, 16, and 18) prior to dose 1 and through 1 month postdose 3 (Month 7). Efficacy was measured starting after the Month 7 visit.

GARDASIL was efficacious in reducing the incidence of CIN (any grade including CIN 2/3); AIS; genital warts; VIN (any grade); and VaIN (any grade) related to vaccine HPV types 6, 11, 16, or 18 in those who were PCR negative and seronegative at baseline (Table 11).

In addition, girls and women who were already infected with 1 or more vaccine-related HPV types prior to vaccination were protected from precancerous cervical lesions and external genital lesions caused by the other vaccine HPV types.

Table 11: Analysis of Efficacy of GARDASIL in the PPE [The PPE population consisted of individuals who received all 3 vaccinations within 1 year of enrollment, did not have major deviations from the study protocol, and were naïve (PCR negative and seronegative) to the relevant HPV type(s) (Types 6, 11, 16, and 18) prior to dose 1 and through 1 month postdose 3 (Month 7).] Population [See Table 14 for analysis of vaccine impact in the general population.] of 16- Through 26-Year-Old Girls and Women for Vaccine HPV Types
Population | GARDASIL |  | AAHS Control |  | % Efficacy (95% CI)
Population | N | Number of cases | N | Number of cases | % Efficacy (95% CI)
HPV 16- or 18-related CIN 2/3 or AIS
Study 1 [Evaluated only the HPV 16 L1 VLP vaccine component of GARDASIL] | 755 | 0 | 750 | 12 | 100.0 (65.1, 100.0)
Study 2 | 231 | 0 | 230 | 1 | 100.0 (-3744.9, 100.0)
Study 3 | 2201 | 0 | 2222 | 36 | 100.0 (89.2, 100.0)
Study 4 | 5306 | 2 | 5262 | 63 | 96.9 (88.2, 99.6)
Combined Protocols [Analyses of the combined trials were prospectively planned and included the use of similar study entry criteria.] | 8493 | 2 | 8464 | 112 | 98.2 (93.5, 99.8)
HPV 16-related CIN 2/3 or AIS
Combined Protocols | 7402 | 2 | 7205 | 93 | 97.9 (92.3, 99.8)
HPV 18-related CIN 2/3 or AIS
Combined Protocols | 7382 | 0 | 7316 | 29 | 100.0 (86.6, 100.0)
HPV 16- or 18-related VIN 2/3
Study 2 | 231 | 0 | 230 | 0 | Not calculated
Study 3 | 2219 | 0 | 2239 | 6 | 100.0 (14.4, 100.0)
Study 4 | 5322 | 0 | 5275 | 4 | 100.0 (-50.3, 100.0)
Combined Protocols | 7772 | 0 | 7744 | 10 | 100.0 (55.5, 100.0)
HPV 16- or 18-related VaIN 2/3
Study 2 | 231 | 0 | 230 | 0 | Not calculated
Study 3 | 2219 | 0 | 2239 | 5 | 100.0 (-10.1, 100.0)
Study 4 | 5322 | 0 | 5275 | 4 | 100.0 (-50.3, 100.0)
Combined Protocols | 7772 | 0 | 7744 | 9 | 100.0 (49.5, 100.0)
HPV 6-, 11-, 16-, or 18-related CIN (CIN 1, CIN 2/3) or AIS
Study 2 | 235 | 0 | 233 | 3 | 100.0 (-138.4, 100.0)
Study 3 | 2241 | 0 | 2258 | 77 | 100.0 (95.1, 100.0)
Study 4 | 5388 | 9 | 5374 | 145 | 93.8 (88.0, 97.2)
Combined Protocols | 7864 | 9 | 7865 | 225 | 96.0 (92.3, 98.2)
HPV 6-, 11-, 16-, or 18-related Genital Warts
Study 2 | 235 | 0 | 233 | 3 | 100.0 (-139.5, 100.0)
Study 3 | 2261 | 0 | 2279 | 58 | 100.0 (93.5, 100.0)
Study 4 | 5404 | 2 | 5390 | 132 | 98.5 (94.5, 99.8)
Combined Protocols | 7900 | 2 | 7902 | 193 | 99.0 (96.2, 99.9)
HPV 6- and 11-related Genital Warts
Combined Protocols | 6932 | 2 | 6856 | 189 | 99.0 (96.2, 99.9)
N = Number of individuals with at least 1 follow-up visit after Month 7
CI = Confidence Interval
Note 1: Point estimates and confidence intervals are adjusted for person-time of follow-up.
Note 2: The first analysis in the table (i.e., HPV 16- or 18-related CIN 2/3, AIS or worse) was the primary endpoint of the vaccine development plan.
Note 3: Table 11 does not include cases due to non-vaccine HPV types.
AAHS Control = Amorphous Aluminum Hydroxyphosphate Sulfate

Prophylactic efficacy against overall cervical and genital disease related to HPV 6, 11, 16, and 18 in an extension phase of Study 2, that included data through Month 60, was noted to be 100% (95% CI: 12.3%, 100.0%) among girls and women in the per protocol population naïve to the relevant HPV types.

GARDASIL was efficacious against HPV disease caused by HPV types 6, 11, 16, and 18 in girls and women who were naïve for those specific HPV types at baseline.

14.2 Prophylactic Efficacy – HPV Types 6, 11, 16, and 18 in Boys and Men 16 through 26 Years of Age

The primary analyses of efficacy were conducted in the per-protocol efficacy (PPE) population. This population consisted of boys and men who received all 3 vaccinations within 1 year of enrollment, did not have major deviations from the study protocol, and were naïve (PCR negative and seronegative) to the relevant HPV type(s) (Types 6, 11, 16, and 18) prior to dose 1 and through 1 month postdose 3 (Month 7). Efficacy was measured starting after the Month 7 visit.

GARDASIL was efficacious in reducing the incidence of genital warts related to vaccine HPV types 6 and 11 in those boys and men who were PCR negative and seronegative at baseline (Table 12). Efficacy against penile/perineal/perianal intraepithelial neoplasia (PIN) grades 1/2/3 or penile/perineal/perianal cancer was not demonstrated as the number of cases was too limited to reach statistical significance.

Table 12: Analysis of Efficacy of GARDASIL in the PPE [The PPE population consisted of individuals who received all 3 vaccinations within 1 year of enrollment, did not have major deviations from the study protocol, and were naïve (PCR negative and seronegative) to the relevant HPV type(s) (Types 6, 11, 16, and 18) prior to dose 1 and through 1 month postdose 3 (Month 7).] Population of 16- Through 26-Year-Old Boys and Men for Vaccine HPV Types
Endpoint | GARDASIL |  | AAHS Control |  | % Efficacy (95% CI)
Endpoint | N [N = Number of individuals with at least 1 follow-up visit after Month 7] | Number of cases | N | Number of cases | % Efficacy (95% CI)
External Genital Lesions HPV 6-, 11-, 16-, or 18- related
External Genital Lesions | 1394 | 3 | 1404 | 32 | 90.6 (70.1, 98.2)
Condyloma | 1394 | 3 | 1404 | 28 | 89.3 (65.3, 97.9)
PIN 1/2/3 | 1394 | 0 | 1404 | 4 | 100.0 (-52.1, 100.0)
CI = Confidence Interval
AAHS Control = Amorphous Aluminum Hydroxyphosphate Sulfate

14.3 Prophylactic Efficacy – Anal Disease Caused by HPV Types 6, 11, 16, and 18 in Boys and Men 16 through 26 Years of Age in the MSM Sub-study

A sub-study of Study 5 evaluated the efficacy of GARDASIL against anal disease (anal intraepithelial neoplasia and anal cancer) in a population of 598 MSM. The primary analyses of efficacy were conducted in the per-protocol efficacy (PPE) population of Study 5.

GARDASIL was efficacious in reducing the incidence of anal intraepithelial neoplasia (AIN) grades 1 (both condyloma and non-acuminate), 2, and 3 related to vaccine HPV types 6, 11, 16, and 18 in those boys and men who were PCR negative and seronegative at baseline (Table 13).

Table 13: Analysis of Efficacy of GARDASIL for Anal Disease in the PPE [The PPE population consisted of individuals who received all 3 vaccinations within 1 year of enrollment, did not have major deviations from the study protocol, and were naïve (PCR negative and seronegative) to the relevant HPV type(s) (Types 6, 11, 16, and 18) prior to dose 1 and through 1 month postdose 3 (month 7).] Population of 16- Through 26-Year-Old Boys and Men in the MSM Sub-study for Vaccine HPV Types
HPV 6-, 11-, 16-, or 18- related Endpoint | GARDASIL |  | AAHS Control |  | % Efficacy (95% CI)
HPV 6-, 11-, 16-, or 18- related Endpoint | N [N = Number of individuals with at least 1 follow-up visit after Month 7] | Number of cases | N | Number of cases | % Efficacy (95% CI)
AIN 1/2/3 | 194 | 5 | 208 | 24 | 77.5 (39.6, 93.3)
AIN 2/3 | 194 | 3 | 208 | 13 | 74.9 (8.8, 95.4)
AIN 1 | 194 | 4 | 208 | 16 | 73.0 (16.3, 93.4)
Condyloma Acuminatum | 194 | 0 | 208 | 6 | 100.0 (8.2, 100.0)
Non-acuminate | 194 | 4 | 208 | 11 | 60.4 (-33.5, 90.8)
CI = Confidence Interval
AAHS Control = Amorphous Aluminum Hydroxyphosphate Sulfate

14.4 Population Impact in Girls and Women 16 through 26 Years of Age

Effectiveness of GARDASIL in Prevention of HPV Types 6-, 11-, 16-, or 18-Related Genital Disease in Girls and Women 16 Through 26 Years of Age, Regardless of Current or Prior Exposure to Vaccine HPV Types

The clinical trials included girls and women regardless of current or prior exposure to vaccine HPV types, and additional analyses were conducted to evaluate the impact of GARDASIL with respect to HPV 6-, 11-, 16-, and 18-related cervical and genital disease in these girls and women. Here, analyses included events arising among girls and women regardless of baseline PCR status and serostatus, including HPV infections that were present at the start of vaccination as well as events that arose from infections that were acquired after the start of vaccination.

The impact of GARDASIL in girls and women regardless of current or prior exposure to a vaccine HPV type is shown in Table 14. Impact was measured starting 1 month postdose 1. Prophylactic efficacy denotes the vaccine's efficacy in girls and women who are naïve (PCR negative and seronegative) to the relevant HPV types at Day 1. Vaccine impact in girls and women who were positive for vaccine HPV infection, as well as vaccine impact among girls and women regardless of baseline vaccine HPV PCR status and serostatus are also presented. The majority of CIN and genital warts, VIN, and VaIN related to a vaccine HPV type detected in the group that received GARDASIL occurred as a consequence of HPV infection with the relevant HPV type that was already present at Day 1.

There was no clear evidence of protection from disease caused by HPV types for which girls and women were PCR positive regardless of serostatus at baseline.

Table 14: Effectiveness of GARDASIL in Prevention of HPV 6, 11, 16, or 18-Related Genital Disease in Girls and Women 16 Through 26 Years of Age, Regardless of Current or Prior Exposure to Vaccine HPV Types
Endpoint | Analysis | GARDASIL or HPV 16 L1 VLP Vaccine |  | AAHS Control |  | % Reduction (95% CI)
Endpoint | Analysis | N | Cases | N | Cases | % Reduction (95% CI)
HPV 16- or 18-related CIN 2/3 or AIS | Prophylactic Efficacy [Includes all individuals who received at least 1 vaccination and who were HPV-naïve (i.e., seronegative and PCR negative) at Day 1 to the vaccine HPV type being analyzed. Case counting started at 1 month postdose 1.] | 9346 | 4 | 9407 | 155 | 97.4 (93.3, 99.3)
HPV 16- or 18-related CIN 2/3 or AIS | HPV 16 and/or HPV 18 Positive at Day 1 [Includes all individuals who received at least 1 vaccination and who were HPV positive or had unknown HPV status at Day 1, to at least one vaccine HPV type. Case counting started at Day 1.] | 2870 | 142 | 2898 | 148 [Out of the 148 AAHS control cases of 16/18 CIN 2/3, 2 women were missing serology or PCR results for Day 1.] | -- [There is no expected efficacy since GARDASIL has not been demonstrated to provide protection against disease from vaccine HPV types to which a person has previously been exposed through sexual activity.]
HPV 16- or 18-related CIN 2/3 or AIS | Girls and Women Regardless of Current or Prior Exposure to HPV 16 or 18 | 9836 | 146 | 9904 | 303 | 51.8 (41.1, 60.7)
HPV 16- or 18-related VIN 2/3 or VaIN 2/3 | Prophylactic Efficacy | 8642 | 1 | 8673 | 34 | 97.0 (82.4, 99.9)
HPV 16- or 18-related VIN 2/3 or VaIN 2/3 | HPV 16 and/or HPV 18 Positive at Day 1 | 1880 | 8 | 1876 | 4 | --
HPV 16- or 18-related VIN 2/3 or VaIN 2/3 | Girls and Women Regardless of Current or Prior Exposure to HPV 16 or 18 [Includes all individuals who received at least 1 vaccination (regardless of baseline HPV status at Day 1). Case counting started at 1 month postdose 1.] | 8955 | 9 | 8968 | 38 | 76.3 (50.0, 89.9)
HPV 6-, 11-, 16-, 18-related CIN (CIN 1, CIN 2/3) or AIS | Prophylactic Efficacy | 8630 | 16 | 8680 | 309 | 94.8 (91.5, 97.1)
HPV 6-, 11-, 16-, 18-related CIN (CIN 1, CIN 2/3) or AIS | HPV 6, HPV 11, HPV 16, and/or HPV 18 Positive at Day 1 | 2466 | 186 [Includes 2 AAHS control women with missing serology/PCR data at Day 1.] | 2437 | 213 | --
HPV 6-, 11-, 16-, 18-related CIN (CIN 1, CIN 2/3) or AIS | Girls and Women Regardless of Current or Prior Exposure to Vaccine HPV Types | 8819 | 202 | 8854 | 522 | 61.5 (54.6, 67.4)
HPV 6-, 11-, 16-, or 18-related Genital Warts | Prophylactic Efficacy | 8761 | 10 | 8792 | 252 | 96.0 (92.6, 98.1)
HPV 6-, 11-, 16-, or 18-related Genital Warts | HPV 6, HPV 11, HPV 16, and/or HPV 18 Positive at Day 1 | 2501 | 51 [Includes 1 woman with missing serology/PCR data at Day 1.] | 2475 | 55 | --
HPV 6-, 11-, 16-, or 18-related Genital Warts | Girls and Women Regardless of Current or Prior Exposure to Vaccine HPV Types | 8955 | 61 | 8968 | 307 | 80.3 (73.9, 85.3)
HPV 6- or 11-related Genital Warts | Prophylactic Efficacy | 7769 | 9 | 7792 | 246 | 96.4 (93.0, 98.4)
HPV 6- or 11-related Genital Warts | HPV 6 and/or HPV 11 Positive at Day 1 | 1186 | 51 | 1176 | 54 | --
HPV 6- or 11-related Genital Warts | Girls and Women Regardless of Current or Prior Exposure to Vaccine HPV Types | 8955 | 60 | 8968 | 300 | 80.1 (73.7, 85.2)
CI = Confidence Interval
N = Number of individuals who have at least one follow-up visit after Day 1
Note 1: The 16- and 18-related CIN 2/3 or AIS composite endpoint included data from studies 1, 2, 3, and 4. All other endpoints only included data from studies 2, 3, and 4.
Note 2: Positive status at Day 1 denotes PCR positive and/or seropositive for the respective type at Day 1.
Note 3: Table 14 does not include disease due to non-vaccine HPV types.
AAHS Control = Amorphous Aluminum Hydroxyphosphate Sulfate

Effectiveness of GARDASIL in Prevention of Any HPV Type Related Genital Disease in Girls and Women 16 Through 26 Years of Age, Regardless of Current or Prior Infection with Vaccine or Non-Vaccine HPV Types

The impact of GARDASIL against the overall burden of dysplastic or papillomatous cervical, vulvar, and vaginal disease regardless of HPV detection, results from a combination of prophylactic efficacy against vaccine HPV types, disease contribution from vaccine HPV types present at time of vaccination, the disease contribution from HPV types not contained in the vaccine, and disease in which HPV was not detected.

Additional efficacy analyses were conducted in 2 populations: (1) a generally HPV-naïve population (negative to 14 common HPV types and had a Pap test that was negative for SIL [Squamous Intraepithelial Lesion] at Day 1), approximating a population of sexually-naïve girls and women and (2) the general study population of girls and women regardless of baseline HPV status, some of whom had HPV-related disease at Day 1.

Among generally HPV-naïve girls and women and among all girls and women in the study population (including girls and women with HPV infection at Day 1), GARDASIL reduced the overall incidence of CIN 2/3 or AIS; of VIN 2/3 or VaIN 2/3; of CIN (any grade) or AIS; and of Genital Warts (Table 15). These reductions were primarily due to reductions in lesions caused by HPV types 6, 11, 16, and 18 in girls and women naïve (seronegative and PCR negative) for the specific relevant vaccine HPV type. Infected girls and women may already have CIN 2/3 or AIS at Day 1 and some will develop CIN 2/3 or AIS during follow-up, either related to a vaccine or non-vaccine HPV type present at the time of vaccination or related to a non-vaccine HPV type not present at the time of vaccination.

Table 15: Effectiveness of GARDASIL in Prevention of Any HPV Type Related Genital Disease in Girls and Women 16 Through 26 Years of Age, Regardless of Current or Prior Infection with Vaccine or Non-Vaccine HPV Types
Endpoints Caused by Vaccine or Non-vaccine HPV Types | Analysis | GARDASIL |  | AAHS Control |  | % Reduction (95% CI)
Endpoints Caused by Vaccine or Non-vaccine HPV Types | Analysis | N | Cases | N | Cases | % Reduction (95% CI)
CIN 2/3 or AIS | Prophylactic Efficacy [Includes all individuals who received at least 1 vaccination and who had a Pap test that was negative for SIL [Squamous Intraepithelial Lesion] at Day 1 and were naïve to 14 common HPV types at Day 1. Case counting started at 1 month postdose 1.] | 4616 | 77 | 4680 | 136 | 42.7 (23.7, 57.3)
CIN 2/3 or AIS | Girls and Women Regardless of Current or Prior Exposure to Vaccine or Non-Vaccine HPV Types [Includes all individuals who received at least 1 vaccination (regardless of baseline HPV status or Pap test result at Day 1). Case counting started at 1 month postdose 1.] | 8559 | 421 | 8592 | 516 | 18.4 (7.0, 28.4)
VIN 2/3 and VaIN 2/3 | Prophylactic Efficacy | 4688 | 7 | 4735 | 31 | 77.1 (47.1, 91.5)
VIN 2/3 and VaIN 2/3 | Girls and Women Regardless of Current or Prior Exposure to Vaccine or Non-Vaccine HPV Types | 8688 | 30 | 8701 | 61 | 50.7 (22.5, 69.3)
CIN (Any Grade) or AIS | Prophylactic Efficacy | 4616 | 272 | 4680 | 390 | 29.7 (17.7, 40.0)
CIN (Any Grade) or AIS | Girls and Women Regardless of Current or Prior Exposure to Vaccine or Non-Vaccine HPV Types | 8559 | 967 | 8592 | 1189 | 19.1 (11.9, 25.8)
Genital Warts | Prophylactic Efficacy | 4688 | 29 | 4735 | 169 | 82.8 (74.3, 88.8)
Genital Warts | Girls and Women Regardless of Current or Prior Exposure to Vaccine or Non-Vaccine HPV Types | 8688 | 132 | 8701 | 350 | 62.5 (54.0, 69.5)
CI = Confidence Interval
AAHS Control = Amorphous Aluminum Hydroxyphosphate Sulfate

14.5 Population Impact in Boys and Men 16 through 26 Years of Age

Effectiveness of GARDASIL in Prevention of HPV Types 6-, 11-, 16-, or 18-Related Anogenital Disease in Boys and Men 16 Through 26 Years of Age, Regardless of Current or Prior Exposure to Vaccine HPV Types

Study 5 included boys and men regardless of current or prior exposure to vaccine HPV types, and additional analyses were conducted to evaluate the impact of GARDASIL with respect to HPV 6-, 11-, 16-, and 18-related anogenital disease in these boys and men. Here, analyses included events arising among boys and men regardless of baseline PCR status and serostatus, including HPV infections that were present at the start of vaccination as well as events that arose from infections that were acquired after the start of vaccination.

The impact of GARDASIL in boys and men regardless of current or prior exposure to a vaccine HPV type is shown in Table 16. Impact was measured starting at Day 1. Prophylactic efficacy denotes the vaccine's efficacy in boys and men who are naïve (PCR negative and seronegative) to the relevant HPV types at Day 1. Vaccine impact in boys and men who were positive for vaccine HPV infection, as well as vaccine impact among boys and men regardless of baseline vaccine HPV PCR status and serostatus are also presented. The majority of anogenital disease related to a vaccine HPV type detected in the group that received GARDASIL occurred as a consequence of HPV infection with the relevant HPV type that was already present at Day 1.

There was no clear evidence of protection from disease caused by HPV types for which boys and men were PCR positive regardless of serostatus at baseline.

Table 16: Effectiveness of GARDASIL in Prevention of HPV Types 6-, 11-, 16-, or 18-Related Anogenital Disease in Boys and Men 16 Through 26 Years of Age, Regardless of Current or Prior Exposure to Vaccine HPV Types
Endpoint | Analysis | GARDASIL |  | AAHS Control |  | % Reduction (95% CI)
Endpoint | Analysis | N | Cases | N | Cases
External Genital Lesions | Prophylactic Efficacy [Includes all individuals who received at least 1 vaccination and who were HPV-naïve (i.e., seronegative and PCR negative) at Day 1 to the vaccine HPV type being analyzed. Case counting started at Day 1.] | 1775 | 13 | 1770 | 54 | 76.3 (56.0, 88.1)
External Genital Lesions | HPV 6, HPV 11, HPV 16, and/or HPV 18 Positive at Day 1 [Includes all individuals who received at least 1 vaccination and who were HPV positive or had unknown HPV status at Day 1, to at least one vaccine HPV type. Case counting started at Day 1.] | 460 | 14 | 453 | 26 | -- [There is no expected efficacy since GARDASIL has not been demonstrated to provide protection against disease from vaccine HPV types to which a person has previously been exposed through sexual activity.]
External Genital Lesions | Boys and Men Regardless of Current or Prior Exposure to Vaccine or Non-Vaccine HPV Types [Includes all individuals who received at least 1 vaccination. Case counting started at Day 1.] | 1943 | 27 | 1937 | 80 | 66.7 (48.0, 79.3)
Condyloma | Prophylactic Efficacy | 1775 | 10 | 1770 | 49 | 80.0 (59.9, 90.9)
Condyloma | HPV 6, HPV 11, HPV 16, and/or HPV 18 Positive at Day 1 | 460 | 14 | 453 | 25 | --
Condyloma | Boys and Men Regardless of Current or Prior Exposure to Vaccine or Non-Vaccine HPV Types | 1943 | 24 | 1937 | 74 | 68.1 (48.8, 80.7)
PIN 1/2/3 | Prophylactic Efficacy | 1775 | 4 | 1770 | 5 | 20.7 (-268.4, 84.3)
PIN 1/2/3 | HPV 6, HPV 11, HPV 16, and/or HPV 18 Positive at Day 1 | 460 | 2 | 453 | 1 | --
PIN 1/2/3 | Boys and Men Regardless of Current or Prior Exposure to Vaccine or Non-Vaccine HPV Types | 1943 | 6 | 1937 | 6 | 0.3 (-272.8, 73.4)
AIN 1/2/3 | Prophylactic Efficacy | 259 | 9 | 261 | 39 | 76.9 (51.4, 90.1)
AIN 1/2/3 | HPV 6, HPV 11, HPV 16, and/or HPV 18 Positive at Day 1 | 103 | 29 | 116 | 38 | --
AIN 1/2/3 | Boys and Men Regardless of Current or Prior Exposure to Vaccine or Non-Vaccine HPV Types | 275 | 38 | 276 | 77 | 50.3 (25.7, 67.2)
AIN 2/3 | Prophylactic Efficacy | 259 | 7 | 261 | 19 | 62.5 (6.9, 86.7)
AIN 2/3 | HPV 6, HPV 11, HPV 16, and/or HPV 18 Positive at Day 1 | 103 | 11 | 116 | 20 | --
AIN 2/3 | Boys and Men Regardless of Current or Prior Exposure to Vaccine or Non-Vaccine HPV Types | 275 | 18 | 276 | 39 | 54.2 (18.0, 75.3)
CI = Confidence Interval
AAHS Control = Amorphous Aluminum Hydroxyphosphate Sulfate

Effectiveness of GARDASIL in Prevention of Any HPV Type Related Anogenital Disease in Boys and Men 16 Through 26 Years of Age, Regardless of Current or Prior Infection with Vaccine or Non-Vaccine HPV Types

The impact of GARDASIL against the overall burden of dysplastic or papillomatous anogenital disease regardless of HPV detection, results from a combination of prophylactic efficacy against vaccine HPV types, disease contribution from vaccine HPV types present at time of vaccination, the disease contribution from HPV types not contained in the vaccine, and disease in which HPV was not detected.

Additional efficacy analyses from Study 5 were conducted in 2 populations: (1) a generally HPV-naïve population that consisted of boys and men who are seronegative and PCR negative to HPV 6, 11, 16, and 18 and PCR negative to HPV 31, 33, 35, 39, 45, 51, 52, 56, 58 and 59 at Day 1, approximating a population of sexually-naïve boys and men and (2) the general study population of boys and men regardless of baseline HPV status, some of whom had HPV-related disease at Day 1.

Among generally HPV-naïve boys and men and among all boys and men in Study 5 (including boys and men with HPV infection at Day 1), GARDASIL reduced the overall incidence of anogenital disease (Table 17). These reductions were primarily due to reductions in lesions caused by HPV types 6, 11, 16, and 18 in boys and men naïve (seronegative and PCR negative) for the specific relevant vaccine HPV type. Infected boys and men may already have anogenital disease at Day 1 and some will develop anogenital disease during follow-up, either related to a vaccine or non-vaccine HPV type present at the time of vaccination or related to a non-vaccine HPV type not present at the time of vaccination.

Table 17: Effectiveness of GARDASIL in Prevention of Any HPV Type Related Anogenital Disease in Boys and Men 16 Through 26 Years of Age, Regardless of Current or Prior Infection with Vaccine or Non-Vaccine HPV Types
Endpoint | Analysis | GARDASIL |  | AAHS Control |  | % Reduction (95% CI)
Endpoint | Analysis | N | Cases | N | Cases
External Genital Lesions | Prophylactic Efficacy [Includes all individuals who received at least 1 vaccination and who were seronegative and PCR negative at enrollment to HPV 6, 11, 16 and 18, and PCR negative at enrollment to HPV 31, 33, 35, 39, 45, 51, 52, 56, 58 and 59. Case counting started at Day 1.] | 1275 | 7 | 1270 | 37 | 81.5 (58.0, 93.0)
External Genital Lesions | Boys and Men Regardless of Current or Prior Exposure to Vaccine or Non-Vaccine HPV Types [Includes all individuals who received at least 1 vaccination. Case counting started at Day 1.] | 1943 | 38 | 1937 | 92 | 59.3 (40.0, 72.9)
Condyloma | Prophylactic Efficacy | 1275 | 5 | 1270 | 33 | 85.2 (61.8, 95.5)
Condyloma | Boys and Men Regardless of Current or Prior Exposure to Vaccine or Non-Vaccine HPV Types | 1943 | 33 | 1937 | 85 | 61.8 (42.3, 75.3)
PIN 1/2/3 | Prophylactic Efficacy | 1275 | 2 | 1270 | 4 | 50.7 (-244.3, 95.5)
PIN 1/2/3 | Boys and Men Regardless of Current or Prior Exposure to Vaccine or Non-Vaccine HPV Types | 1943 | 8 | 1937 | 7 | -13.9 (-269.0, 63.9)
AIN 1/2/3 | Prophylactic Efficacy | 129 | 12 | 126 | 28 | 54.9 (8.4, 79.1)
AIN 1/2/3 | Boys and Men Regardless of Current or Prior Exposure to Vaccine or Non-Vaccine HPV Types | 275 | 74 | 276 | 103 | 25.7 (-1.1, 45.6)
AIN 2/3 | Prophylactic Efficacy | 129 | 8 | 126 | 18 | 52.5 (-14.8, 82.1)
AIN 2/3 | Boys and Men Regardless of Current or Prior Exposure to Vaccine or Non-Vaccine HPV Types | 275 | 44 | 276 | 59 | 24.3 (-13.8, 50.0)
CI = Confidence Interval
AAHS Control = Amorphous Aluminum Hydroxyphosphate Sulfate

14.6 Overall Population Impact

The subject characteristics (e.g., lifetime sex partners, geographic distribution of the subjects) influence the HPV prevalence of the population and therefore the population benefit can vary widely.

The overall efficacy of GARDASIL will vary with the baseline prevalence of HPV infection and disease, the incidence of infections against which GARDASIL has shown protection, and those infections against which GARDASIL has not been shown to protect.

The efficacy of GARDASIL for HPV types not included in the vaccine (i.e., cross-protective efficacy) is a component of the overall impact of the vaccine on rates of disease caused by HPV. Cross-protective efficacy was not demonstrated against disease caused by non-vaccine HPV types in the combined database of the Study 3 and Study 4 trials.

GARDASIL does not protect against genital disease not related to HPV. One woman who received GARDASIL in Study 3 developed an external genital well-differentiated squamous cell carcinoma at Month 24. No HPV DNA was detected in the lesion or in any other samples taken throughout the study.

In 18,150 girls and women enrolled in Study 2, Study 3, and Study 4, GARDASIL reduced definitive cervical therapy procedures by 23.9% (95% CI: 15.2%, 31.7%).

14.7 Studies in Women 27 through 45 Years of Age

Study 6 evaluated efficacy in 3253 women 27 through 45 years of age based on a combined endpoint of HPV 6-, 11-, 16- or 18-related persistent infection, genital warts, vulvar and vaginal dysplastic lesions of any grade, CIN of any grade, AIS, and cervical cancer. These women were randomized 1:1 to receive either GARDASIL or AAHS control. The efficacy for the combined endpoint was driven primarily by prevention of persistent infection. There was no statistically significant efficacy demonstrated for CIN 2/3, AIS, or cervical cancer. In post hoc analyses conducted to assess the impact of GARDASIL on the individual components of the combined endpoint, the results in the population of women naïve to the relevant HPV type at baseline were as follows: prevention of HPV 6-, 11-, 16- or 18-related persistent infection (80.5% [95% CI: 68.3, 88.6]), prevention of HPV 6-, 11-, 16- or 18-related CIN (any grade) (85.8% [95% CI: 52.4, 97.3]), and prevention of HPV 6-, 11-, 16- or 18-related genital warts (87.6% [95% CI: 7.3, 99.7]).

Efficacy for disease endpoints was diminished in a population impact assessment of women who were vaccinated regardless of baseline HPV status (full analysis set). In the full analysis set (FAS), efficacy was not demonstrated for the following endpoints: prevention of HPV 16- and 18-related CIN 2/3, AIS, or cervical cancer and prevention of HPV 6- and 11-related condyloma. No efficacy was demonstrated against CIN 2/3, AIS, or cervical cancer in the general population irrespective of HPV type (FAS any type analysis).

14.8 Immunogenicity

Assays to Measure Immune Response

The minimum anti-HPV titer that confers protective efficacy has not been determined.

Because there were few disease cases in individuals naïve (PCR negative and seronegative) to vaccine HPV types at baseline in the group that received GARDASIL, it has not been possible to establish minimum anti-HPV 6, anti-HPV 11, anti-HPV 16, and anti-HPV 18 antibody levels that protect against clinical disease caused by HPV 6, 11, 16, and/or 18.

The immunogenicity of GARDASIL was assessed in 23,951 9- through 45-year-old girls and women (GARDASIL N = 12,634; AAHS control or saline placebo N = 11,317) and 5417 9- through 26-year-old boys and men (GARDASIL N = 3109; AAHS control or saline placebo N = 2308).

Type-specific immunoassays with type-specific standards were used to assess immunogenicity to each vaccine HPV type. These assays measured antibodies against neutralizing epitopes for each HPV type. The scales for these assays are unique to each HPV type; thus, comparisons across types and to other assays are not appropriate.

Immune Response to GARDASIL

The primary immunogenicity analyses were conducted in a per-protocol immunogenicity (PPI) population. This population consisted of individuals who were seronegative and PCR negative to the relevant HPV type(s) at enrollment, remained HPV PCR negative to the relevant HPV type(s) through 1 month postdose 3 (Month 7), received all 3 vaccinations, and did not deviate from the study protocol in ways that could interfere with the effects of the vaccine.

Immunogenicity was measured by (1) the percentage of individuals who were seropositive for antibodies against the relevant vaccine HPV type, and (2) the Geometric Mean Titer (GMT).

In clinical studies in 16- through 26-year-old girls and women, 99.8%, 99.8%, 99.8%, and 99.4% who received GARDASIL became anti-HPV 6, anti-HPV 11, anti-HPV 16, and anti-HPV 18 seropositive, respectively, by 1 month postdose 3 across all age groups tested.

In clinical studies in 27- through 45-year-old women, 98.2%, 97.9%, 98.6%, and 97.1% who received GARDASIL became anti-HPV 6, anti-HPV 11, anti-HPV 16, and anti-HPV 18 seropositive, respectively, by 1 month postdose 3 across all age groups tested.

In clinical studies in 16- through 26-year-old boys and men, 98.9%, 99.2%, 98.8%, and 97.4% who received GARDASIL became anti-HPV 6, anti-HPV 11, anti-HPV 16, and anti-HPV 18 seropositive, respectively, by 1 month postdose 3 across all age groups tested.

Across all populations, anti-HPV 6, anti-HPV 11, anti-HPV 16, and anti-HPV 18 GMTs peaked at Month 7 (Table 18 and Table 19). GMTs declined through Month 24 and then stabilized through Month 36 at levels above baseline. Tables 20 and 21 display the persistence of anti-HPV cLIA geometric mean titers by gender and age group. The duration of immunity following a complete schedule of immunization with GARDASIL has not been established.

Table 18: Summary of Month 7 Anti-HPV cLIA Geometric Mean Titers in the PPI [The PPI population consisted of individuals who received all 3 vaccinations within pre-defined day ranges, did not have major deviations from the study protocol, met predefined criteria for the interval between the Month 6 and Month 7 visit, and were naïve (PCR negative and seronegative) to the relevant HPV type(s) (types 6, 11, 16, and 18) prior to dose 1 and through 1 month Postdose 3 (Month 7).] Population of Girls and Women
Population | N [Number of individuals randomized to the respective vaccination group who received at least 1 injection.] | n [Number of individuals contributing to the analysis.] | % Seropositive (95% CI) | GMT (95% CI) mMU [mMU = milli-Merck Units] /mL
Anti-HPV 6
9- through 15-year-old girls | 1122 | 917 | 99.9 (99.4, 100.0) | 929.2 (874.6, 987.3)
16- through 26-year-old girls and women | 9859 | 3329 | 99.8 (99.6, 99.9) | 545.0 (530.1, 560.4)
27- through 34-year-old women | 667 | 439 | 98.4 (96.7, 99.4) | 435.6 (393.4, 482.4)
35- through 45-year-old women | 957 | 644 | 98.1 (96.8, 99.0) | 397.3 (365.2, 432.2)
Anti-HPV 11
9- through 15-year-old girls | 1122 | 917 | 99.9 (99.4, 100.0) | 1304.6 (1224.7, 1389.7)
16- through 26-year-old girls and women | 9859 | 3353 | 99.8 (99.5, 99.9) | 748.9 (726.0, 772.6)
27- through 34-year-old women | 667 | 439 | 98.2 (96.4, 99.2) | 577.9 (523.8, 637.5)
35- through 45-year-old women | 957 | 644 | 97.7 (96.2, 98.7) | 512.8 (472.9, 556.1)
Anti-HPV 16
9- through 15-year-old girls | 1122 | 915 | 99.9 (99.4, 100.0) | 4918.5 (4556.6, 5309.1)
16- through 26-year-old girls and women | 9859 | 3249 | 99.8 (99.6, 100.0) | 2409.2 (2309.0, 2513.8)
27- through 34-year-old women | 667 | 435 | 99.3 (98.0, 99.9) | 2342.5 (2119.1, 2589.6)
35- through 45-year-old women | 957 | 657 | 98.2 (96.8, 99.1) | 2129.5 (1962.7, 2310.5)
Anti-HPV 18
9- through 15-year-old girls | 1122 | 922 | 99.8 (99.2, 100.0) | 1042.6 (967.6, 1123.3)
16- through 26-year-old girls and women | 9859 | 3566 | 99.4 (99.1, 99.7) | 475.2 (458.8, 492.1)
27- through 34-year-old women | 667 | 501 | 98.0 (96.4, 99.0) | 385.8 (347.6, 428.1)
35- through 45-year-old women | 957 | 722 | 96.4 (94.8, 97.6) | 324.6 (297.6, 354.0)
cLIA = Competitive Luminex Immunoassay
CI = Confidence Interval
GMT = Geometric Mean Titers

Table 19: Summary of Month 7 Anti-HPV cLIA Geometric Mean Titers in the PPI [The PPI population consisted of individuals who received all 3 vaccinations within pre-defined day ranges, did not have major deviations from the study protocol, met predefined criteria for the interval between the Month 6 and Month 7 visit, and were naïve (PCR negative and seronegative) to the relevant HPV type(s) (types 6, 11, 16, and 18) prior to dose 1 and through 1 month Postdose 3 (Month 7).] Population of Boys and Men
Population | N [Number of individuals randomized to the respective vaccination group who received at least 1 injection.] | n [Number of individuals contributing to the analysis.] | % Seropositive (95% CI) | GMT (95% CI) mMU [mMU = milli-Merck Units] /mL
Anti-HPV 6
9- through 15-year-old boys | 1072 | 884 | 99.9 (99.4, 100.0) | 1037.5 (963.5, 1117.3)
16- through 26-year-old boys and men | 2026 | 1093 | 98.9 (98.1, 99.4) | 447.8 (418.9, 478.6)
Anti-HPV 11
9- through 15-year-old boys | 1072 | 885 | 99.9 (99.4, 100.0) | 1386.8 (1298.5, 1481.0)
16- through 26-year-old boys and men | 2026 | 1093 | 99.2 (98.4, 99.6) | 624.3 (588.4, 662.3)
Anti-HPV 16
9- through 15-year-old boys | 1072 | 882 | 99.8 (99.2, 100.0) | 6056.5 (5601.3, 6548.7)
16- through 26-year-old boys and men | 2026 | 1136 | 98.8 (97.9, 99.3) | 2403.3 (2243.4, 2574.6)
Anti-HPV 18
9- through 15-year-old boys | 1072 | 887 | 99.8 (99.2, 100) | 1357.4 (1249.4, 1474.7)
16- through 26-year-old boys and men | 2026 | 1175 | 97.4 (96.3, 98.2) | 402.6 (374.6, 432.7)
cLIA = Competitive Luminex Immunoassay
CI = Confidence Interval
GMT = Geometric Mean Titers

Table 20: Persistence of Anti-HPV cLIA Geometric Mean Titers in 9- Through 45-Year-Old Girls and Women
Assay (cLIA)/ Time Point | 9- to 15-Year-Old Girls (N [N = Number of individuals randomized in the respective group who received at least 1 injection.] = 1122) |  | 16- to 26-Year-Old Girls and Women (N = 9859) |  | 27- to 34-Year-Old Women (N = 667) |  | 35- to 45-Year-Old Women (N = 957)
Assay (cLIA)/ Time Point | n [n = Number of individuals in the indicated immunogenicity population.] | GMT (95% CI) mMU [mMU = milli-Merck Units] /mL | n | GMT (95% CI) mMU/mL | n | GMT (95% CI) mMU/mL | n | GMT (95% CI) mMU/mL
Anti-HPV 6
Month 07 | 917 | 929.2 (874.6, 987.3) | 3329 | 545.0 (530.1, 560.4) | 439 | 435.6 (393.4, 482.4) | 644 | 397.3 (365.2, 432.2)
Month 24 | 214 | 156.1 (135.6, 179.6) | 2788 | 109.1 (105.2, 113.1) | 421 | 70.7 (63.8, 78.5) | 628 | 69.3 (63.7, 75.4)
Month 36 [Month 37 for 9- to 15-year-old girls. No serology samples were collected at this time point for 16- to 26-year-old girls and women.] | 356 | 129.4 (115.6, 144.8) | - | - | 399 | 79.5 (72.0, 87.7) | 618 | 81.1 (75.0, 87.8)
Month 48 [Month 48/End-of-study visits for 16- to 26-year-old girls and women were generally scheduled earlier than Month 48. Mean visit timing was Month 44. The studies in 9- to 15-year-old girls were planned to end prior to 48 months and therefore no serology samples were collected.] | - | - | 2514 | 73.8 (70.9, 76.8) | 391 | 58.8 (52.9, 65.3) | 616 | 62.0 (57.0, 67.5)
Anti-HPV 11
Month 07 | 917 | 1304.6 (1224.7, 1389.7) | 3353 | 748.9 (726.0, 772.6) | 439 | 577.9 (523.8, 637.5) | 644 | 512.8 (472.9, 556.1)
Month 24 | 214 | 218.0 (188.3, 252.4) | 2817 | 137.1 (132.1, 142.3) | 421 | 79.3 (71.5, 87.8) | 628 | 73.4 (67.4, 79.8)
Month 36 | 356 | 148.0 (131.1, 167.1) | - | - | 399 | 81.8 (74.3, 90.1) | 618 | 77.4 (71.6, 83.6)
Month 48 | - | - | 2538 | 89.4 (85.9, 93.1) | 391 | 67.4 (60.9, 74.7) | 616 | 62.7 (57.8, 68.0)
Anti-HPV 16
Month 07 | 915 | 4918.5 (4556.6, 5309.1) | 3249 | 2409.2 (2309.0, 2513.8) | 435 | 2342.5 (2119.1, 2589.6) | 657 | 2129.5 (1962.7, 2310.5)
Month 24 | 211 | 944.2 (804.4, 1108.3) | 2721 | 442.6 (425.0, 460.9) | 416 | 285.9 (254.4, 321.2) | 642 | 271.4 (247.1, 298.1)
Month 36 | 353 | 642.2 (562.8, 732.8) | - | - | 399 | 291.5 (262.5, 323.8) | 631 | 276.7 (254.5, 300.8)
Month 48 | - | - | 2474 | 326.2 (311.8, 341.3) | 394 | 211.8 (189.5, 236.8) | 628 | 192.8 (176.5, 210.6)
Anti-HPV 18
Month 07 | 922 | 1042.6 (967.6, 1123.3) | 3566 | 475.2 (458.8, 492.1) | 501 | 385.8 (347.6, 428.1) | 722 | 324.6 (297.6, 354.0)
Month 24 | 214 | 137.7 (114.8, 165.1) | 3002 | 50.8 (48.2, 53.5) | 478 | 31.8 (28.1, 36.0) | 705 | 26.0 (23.5, 28.8)
Month 36 | 357 | 87.0 (74.8, 101.2) | - | - | 453 | 32.1 (28.5, 36.3) | 689 | 27.0 (24.5, 29.8)
Month 48 | - | - | 2710 | 33.2 (31.5, 35.0) | 444 | 25.2 (22.3, 28.5) | 688 | 21.2 (19.2, 23.4)
cLIA = Competitive Luminex Immunoassay
CI = Confidence Interval
GMT = Geometric Mean Titers

Table 21: Persistence of Anti-HPV cLIA Geometric Mean Titers in 9- Through 26-Year-Old Boys and Men
Assay (cLIA)/ Time Point | 9- to 15-Year-Old Boys (N [N = Number of individuals randomized in the respective group who received at least 1 injection.] = 1072) |  | 16- to 26-Year-Old Boys and Men (N = 2026)
Assay (cLIA)/ Time Point | n [n = Number of individuals in the indicated immunogenicity population.] | GMT (95% CI) mMU [mMU = milli-Merck Units] /mL | n | GMT (95% CI) mMU/mL
Anti-HPV 6
Month 07 | 884 | 1037.5 (963.5, 1117.3) | 1094 | 447.2 (418.4, 477.9)
Month 24 | 323 | 134.1 (119.5, 150.5) | 907 | 80.3 (74.9, 86.0)
Month 36 [Month 36 time point for 16- to 26-year-old boys and men; Month 37 for 9- to 15-year-old boys.] | 342 | 126.6 (111.9, 143.2) | 654 | 72.4 (68.0, 77.2)
Month 48 [The studies in 9- to 15-year-old boys and girls and 16- to 26-year-old boys and men were planned to end prior to 48 months and therefore no serology samples were collected.] | - | - | - | -
Anti-HPV 11
Month 07 | 885 | 1386.8 (1298.5, 1481.0) | 1094 | 624.5 (588.6, 662.5)
Month 24 | 324 | 188.5 (168.4, 211.1) | 907 | 94.6 (88.4, 101.2)
Month 36 | 342 | 148.8 (131.1, 169.0) | 654 | 80.3 (75.7, 85.2)
Month 48 | - | - | - | -
Anti-HPV 16
Month 07 | 882 | 6056.5 (5601.4, 6548.6) | 1137 | 2401.5 (2241.8, 2572.6)
Month 24 | 322 | 938.2 (825.0, 1067.0) | 938 | 347.7 (322.5, 374.9)
Month 36 | 341 | 708.8 (613.9, 818.3) | 672 | 306.7 (287.5, 327.1)
Month 48 | - | - | - | -
Anti-HPV 18
Month 07 | 887 | 1357.4 (1249.4, 1474.7) | 1176 | 402.6 (374.6, 432.6)
Month 24 | 324 | 131.9 (112.1, 155.3) | 967 | 38.7 (35.2, 42.5)
Month 36 | 343 | 113.0 (94.7, 135.0) | 690 | 33.4 (30.9, 36.1)
Month 48 | - | - | - | -
cLIA = Competitive Luminex Immunoassay
CI = Confidence Interval
GMT = Geometric Mean Titers

Tables 18 and 19 display the Month 7 immunogenicity data for girls and women and boys and men. Anti-HPV responses 1 month postdose 3 among 9- through 15-year-old adolescent girls were non-inferior to anti-HPV responses in 16- through 26-year-old girls and women in the combined database of immunogenicity studies for GARDASIL. Anti-HPV responses 1 month postdose 3 among 9- through 15-year-old adolescent boys were non-inferior to anti-HPV responses in 16- through 26-year-old boys and men in Study 5.

On the basis of this immunogenicity bridging, the efficacy of GARDASIL in 9- through 15-year-old adolescent girls and boys is inferred.

GMT Response to Variation in Dosing Regimen in 18- Through 26-Year-Old Women

Girls and women evaluated in the PPE population of clinical studies received all 3 vaccinations within 1 year of enrollment. An analysis of immune response data suggests that flexibility of ±1 month for Dose 2 (i.e., Month 1 to Month 3 in the vaccination regimen) and flexibility of ±2 months for Dose 3 (i.e., Month 4 to Month 8 in the vaccination regimen) do not impact the immune responses to GARDASIL.

Duration of the Immune Response to GARDASIL

The duration of immunity following a complete schedule of immunization with GARDASIL has not been established. The peak anti-HPV GMTs for HPV types 6, 11, 16, and 18 occurred at Month 7. Anti-HPV GMTs for HPV types 6, 11, 16, and 18 were similar between measurements at Month 24 and Month 60 in Study 2.

14.9 Long-Term Follow-Up Studies

The protection of GARDASIL against HPV-related disease continues to be studied over time in populations including adolescents (boys and girls) and women who were enrolled in the Phase 3 studies.

Persistence of Effectiveness

An extension of Study 4 used national healthcare registries in Denmark, Iceland, Norway, and Sweden to monitor endpoint cases of HPV 6-, 11-, 16-, or 18-related CIN (any grade), AIS, cervical cancer, vulvar cancer, or vaginal cancer among 2,650 girls and women 16 through 23 years of age at enrollment who were randomized to vaccination with GARDASIL and consented to be followed in the extension study. An interim analysis of the per-protocol effectiveness population included 1,902 subjects who completed the GARDASIL vaccination series within one year, were naïve to the relevant HPV type through 1 month postdose 3, had no protocol violations, and had follow-up data available. The median follow-up from initial vaccination was 6.7 years with a range of 2.8 to 8.4 years. No cases of HPV 6-, 11-, 16-, or 18-related CIN (any grade), AIS, cervical cancer, vulvar cancer, or vaginal cancer were observed over a total of 5,765 person-years at risk.

An extension of a Phase 3 study (Study 7) in which 614 girls and 565 boys 9 through 15 years of age at enrollment were randomized to vaccination with GARDASIL actively followed subjects for endpoint cases of HPV 6-, 11-, 16-, or 18-related persistent infection, CIN (any grade), AIS, VIN, VaIN, cervical cancer, vulvar cancer, vaginal cancer, and genital lesions from the initiation of sexual activity or age 16 onwards. An interim analysis of the per-protocol effectiveness population included 246 girls and 168 boys who completed the GARDASIL vaccination series within one year, were seronegative to the relevant HPV type at initiation of the vaccination series, and had not initiated sexual activity prior to receiving the third dose of GARDASIL. The median follow-up, from the first dose of vaccine, was 7.2 years with a range of 0.5 to 8.5 years. No cases of persistent infection of at least 12 months' duration and no cases of HPV 6-, 11-, 16-, or 18-related CIN (any grade), AIS, VIN, VaIN, cervical cancer, vulvar cancer, vaginal cancer, or genital lesions were observed over a total 1,105 person-years at risk. There were 4 cases of HPV 6-, 11-, 16-, or 18-related persistent infection of at least 6 months' duration, including 3 cases related to HPV 16 and 1 case related to HPV 6, none of which persisted to 12 months' duration.

Persistence of the Immune Response

The interim reports of the two extension studies described above included analyses of type-specific anti-HPV antibody titers at 9 years postdose 1 for girls and women 16 through 23 years of age at enrollment (range of 1,178 to 1,331 subjects with evaluable data across HPV types) and at 8 years postdose 1 for boys and girls 9 through 15 years of age at enrollment (range of 436 to 440 subjects with evaluable data across HPV types). Anti-HPV 6, 11, 16, and 18 GMTs as measured by cLIA were decreased compared with corresponding values at earlier time points, but the proportions of seropositive subjects ranged from 88.4% to 94.4% for anti-HPV 6, from 89.1% to 95.5% for anti-HPV 11, from 96.8% to 99.1% for anti-HPV 16, and from 60.0% to 64.1% for anti-HPV 18.

14.10 Studies with RECOMBIVAX HB [hepatitis B vaccine (recombinant)]

The safety and immunogenicity of co-administration of GARDASIL with RECOMBIVAX HB [hepatitis B vaccine (recombinant)] (same visit, injections at separate sites) were evaluated in a randomized, double-blind, study of 1871 women aged 16 through 24 years at enrollment. The race distribution of the girls and women in the clinical trial was as follows: 61.6% White; 1.6% Hispanic (Black and White); 23.8% Other; 11.9% Black; 0.8% Asian; and 0.3% American Indian.

Subjects either received GARDASIL and RECOMBIVAX HB (n = 466), GARDASIL and RECOMBIVAX HB-matched placebo (n = 468), RECOMBIVAX HB and GARDASIL-matched placebo (n = 467) or RECOMBIVAX-matched placebo and GARDASIL-matched placebo (n = 470) at Day 1, Month 2 and Month 6. Immunogenicity was assessed for all vaccines 1 month post completion of the vaccination series.

Concomitant administration of GARDASIL with RECOMBIVAX HB [hepatitis B vaccine (recombinant)] did not interfere with the antibody response to any of the vaccine antigens when GARDASIL was given concomitantly with RECOMBIVAX HB or separately.

14.11 Studies with Menactra [Meningococcal (Groups A, C, Y and W-135) Polysaccharide Diphtheria Toxoid Conjugate Vaccine] and Adacel [Tetanus Toxoid, Reduced Diphtheria Toxoid and Acellular Pertussis Vaccine Adsorbed (Tdap)]

The safety and immunogenicity of co-administration of GARDASIL with Menactra [Meningococcal (Groups A, C, Y and W-135) Polysaccharide Diphtheria Toxoid Conjugate Vaccine] and Adacel [Tetanus Toxoid, Reduced Diphtheria Toxoid and Acellular Pertussis Vaccine Adsorbed (Tdap)] (same visit, injections at separate sites) were evaluated in an open-labeled, randomized, controlled study of 1040 boys and girls 11 through 17 years of age at enrollment. The race distribution of the subjects in the clinical trial was as follows: 77.7% White; 6.8% Hispanic (Black and White); 1.4% Multi-racial; 12.3% Black; 1.2% Asian; 0.2% Indian; and 0.4% American Indian.

One group received GARDASIL in one limb and both Menactra and Adacel, as separate injections, in the opposite limb concomitantly on Day 1 (n = 517). The second group received the first dose of GARDASIL on Day 1 in one limb then Menactra and Adacel, as separate injections, at Month 1 in the opposite limb (n = 523). Subjects in both vaccination groups received the second dose of GARDASIL at Month 2 and the third dose at Month 6. Immunogenicity was assessed for all vaccines 1 month post completion of the vaccination series (1 dose for Menactra and Adacel and 3 doses for GARDASIL).

Concomitant administration of GARDASIL with Menactra [Meningococcal (Groups A, C, Y and W-135) Polysaccharide Diphtheria Toxoid Conjugate Vaccine] and Adacel [Tetanus Toxoid, Reduced Diphtheria Toxoid and Acellular Pertussis Vaccine Adsorbed (Tdap)] did not interfere with the antibody response to any of the vaccine antigens when GARDASIL was given concomitantly with Menactra and Adacel or separately.

16 HOW SUPPLIED/STORAGE AND HANDLING

All presentations for GARDASIL contain a suspension of 120 mcg L1 protein from HPV types 6, 11, 16, and 18 in a 0.5-mL dose. GARDASIL is supplied in vials and syringes.

Carton of one 0.5-mL single-dose vial. NDC 0006-4045-00.

Carton of ten 0.5-mL single-dose vials. NDC 0006-4045-41.

Carton of six 0.5-mL single-dose prefilled Luer-Lok® syringes with tip caps. NDC 0006-4109-09.

Carton of ten 0.5-mL single-dose prefilled Luer-Lok® syringes with tip caps. NDC 0006-4109-02.

STORAGE AND HANDLING

Store refrigerated at 2 to 8°C (36 to 46°F). Do not freeze. Protect from light.

GARDASIL should be administered as soon as possible after being removed from refrigeration.

GARDASIL can be out of refrigeration (at temperatures at or below 25°C/77°F), for a total time of not more than 72 hours.

17 PATIENT COUNSELING INFORMATION

Advise the patient to read the FDA-approved patient labeling (Patient Information).

Inform the patient, parent, or guardian:

- Vaccination does not eliminate the necessity for women to continue to undergo recommended cervical cancer screening. Women who receive GARDASIL should continue to undergo cervical cancer screening per standard of care.
- Recipients of GARDASIL should not discontinue anal cancer screening if it has been recommended by a health care provider.
- GARDASIL has not been demonstrated to provide protection against disease from vaccine and non-vaccine HPV types to which a person has previously been exposed through sexual activity.
- Since syncope has been reported following vaccination sometimes resulting in falling with injury, observation for 15 minutes after administration is recommended.
- Vaccine information is required to be given with each vaccination to the patient, parent, or guardian.
- Information regarding benefits and risks associated with vaccination.
- GARDASIL is not recommended for use in pregnant women.
- Importance of completing the immunization series unless contraindicated.
- Report any adverse reactions to their health care provider.

Manuf. and Dist. by: Merck Sharp & Dohme LLC
Rahway, NJ 07065, USA

For patent information: www.msd.com/research/patent

The trademarks depicted herein are owned by their respective companies.

Copyright © 2006-2025 Merck & Co., Inc., Rahway, NJ, USA, and its affiliates.
All rights reserved.

uspi-v501-i-2504r023

Printed in USA

Patient Information about GARDASIL® (pronounced "gard-Ah-sill")
[Human Papillomavirus Quadrivalent (Types 6, 11, 16, and 18) Vaccine, Recombinant]

Read this information with care before getting GARDASIL. You (the person getting GARDASIL) will need 3 doses of the vaccine. It is important to read this leaflet when you get each dose. This leaflet does not take the place of talking with your health care provider about GARDASIL.

What is GARDASIL?

GARDASIL is a vaccine that is used for girls and women 9 through 26 years of age to help protect against the following diseases caused by Human Papillomavirus (HPV):

- Cervical cancer
- Vulvar and vaginal cancers
- Anal cancer
- Genital warts
- Precancerous cervical, vaginal, vulvar, and anal lesions

GARDASIL is used for boys and men 9 through 26 years of age to help protect against the following diseases caused by HPV:

- Anal cancer
- Genital warts
- Precancerous anal lesions
  - The diseases listed above have many causes, and GARDASIL only protects against diseases caused by certain kinds of HPV (called Type 6, Type 11, Type 16, and Type 18). Most of the time, these 4 types of HPV are responsible for the diseases listed above.
  - GARDASIL cannot protect you from a disease that is caused by other types of HPV, other viruses, or bacteria.
  - GARDASIL does not treat HPV infection.
  - You cannot get HPV or any of the above diseases from GARDASIL.

What important information about GARDASIL should I know?

- You should continue to get routine cervical cancer screening.
- GARDASIL may not fully protect everyone who gets the vaccine.
- GARDASIL will not protect against HPV types that you already have.

Who should not get GARDASIL?

You should not get GARDASIL if you have, or have had:

- an allergic reaction after getting a dose of GARDASIL.
- a severe allergic reaction to yeast, amorphous aluminum hydroxyphosphate sulfate, polysorbate 80.

What should I tell my health care provider before getting GARDASIL?

Tell your health care provider if you:

- are pregnant or planning to get pregnant. GARDASIL is not recommended for use in pregnant women.
- have immune problems, like HIV infection, cancer, or you take medicines that affect your immune system.
- have a fever over 100°F (37.8°C).
- had an allergic reaction to another dose of GARDASIL.
- take any medicines, even those you can buy over the counter.

Your health care provider will help decide if you should get the vaccine.

How is GARDASIL given?

GARDASIL is an injection that is usually given in the arm muscle. You will need 3 injections given on the following schedule:

- Dose 1: at a date you and your health care provider choose.
- Dose 2: 2 months after Dose 1.
- Dose 3: 6 months after Dose 1.

Fainting can happen after getting GARDASIL. Sometimes people who faint can fall and hurt themselves. For this reason, your health care provider may ask you to sit or lie down for 15 minutes after you get GARDASIL. Some people who faint might shake or become stiff. This may require evaluation or treatment by your health care provider.

Make sure that you get all 3 doses on time so that you get the best protection. If you miss a dose, talk to your health care provider.

Can other vaccines and medications be given at the same time as GARDASIL?

GARDASIL can be given at the same time as RECOMBIVAX HB®1 [hepatitis B vaccine (recombinant)] or Menactra [Meningococcal (Groups A, C, Y and W-135) Polysaccharide Diphtheria Toxoid Conjugate Vaccine] and Adacel [Tetanus Toxoid, Reduced Diphtheria Toxoid and Acellular Pertussis Vaccine Adsorbed (Tdap)].

What are the possible side effects of GARDASIL?

The most common side effects with GARDASIL are:

- pain, swelling, itching, bruising, and redness at the injection site
- headache
- fever
- nausea
- dizziness
- vomiting
- fainting

There was no increase in side effects when GARDASIL was given at the same time as RECOMBIVAX HB [hepatitis B vaccine (recombinant)].

There was more injection-site swelling at the injection site for GARDASIL when GARDASIL was given at the same time as Menactra [Meningococcal (Groups A, C, Y and W-135) Polysaccharide Diphtheria Toxoid Conjugate Vaccine] and Adacel [Tetanus Toxoid, Reduced Diphtheria Toxoid and Acellular Pertussis Vaccine Adsorbed (Tdap)].

Tell your health care provider if you have any of the following problems because these may be signs of an allergic reaction:

- difficulty breathing
- wheezing (bronchospasm)
- hives
- rash

Tell your health care provider if you have:

- swollen glands (neck, armpit, or groin)
- joint pain
- unusual tiredness, weakness, or confusion
- chills
- generally feeling unwell
- leg pain
- shortness of breath
- chest pain
- aching muscles
- muscle weakness
- seizure
- bad stomach ache
- bleeding or bruising more easily than normal
- skin infection
- lump where you got the injection

Contact your health care provider right away if you get any symptoms that concern you, even several months after getting the vaccine.

For a more complete list of side effects, ask your health care provider.

What are the ingredients in GARDASIL?

The ingredients are proteins of HPV Types 6, 11, 16, and 18, amorphous aluminum hydroxyphosphate sulfate, yeast protein, sodium chloride, L-histidine, polysorbate 80, sodium borate, and water for injection.

This leaflet is a summary of information about GARDASIL. If you would like more information, please talk to your health care provider or visit www.gardasil.com.

Manufactured and Distributed by: Merck Sharp & Dohme LLC
Rahway, NJ 07065, USA

Copyright © 2006-2025 Merck & Co., Inc., Rahway, NJ, USA, and its affiliates.
All rights reserved.

usppi-v501-i-2504r018

Revised: April 2025

PRINCIPAL DISPLAY PANEL - 0.5 mL Vial Carton

NDC 0006-4045-00
1 Single-dose Vial 0.5 mL

REFRIGERATE

[Human Papillomavirus
Quadrivalent
(Types 6, 11, 16, and 18)
Vaccine, Recombinant]
GARDASIL®

0.5 mL dose contains human
papillomavirus L1 protein of each
type adsorbed on amorphous
aluminum hydroxyphosphate
sulfate adjuvant as follows:
Type 6 (20 mcg), Type 11 (40 mcg),
Type 16 (40 mcg), Type 18 (20 mcg)

Vaccine is prepared from
fermentation cultures of a
recombinant strain of yeast
Saccharomyces cerevisiae
containing the genes for the
human papillomavirus L1 protein
of each type (6, 11, 16, 18).

Contains no preservative
or antibiotics.

Rx only

PRINCIPAL DISPLAY PANEL - 10 Single-Dose 0.5 mL Syringe Carton

NDC 0006-4109-02
10 Single-dose 0.5-mL Syringes

REFRIGERATE

[Human Papillomavirus Quadrivalent
(Types 6, 11, 16, and 18)
Vaccine, Recombinant]
GARDASIL®

Each 0.5-mL dose contains human papillomavirus L1 protein of
each type adsorbed on amorphous aluminum hydroxyphosphate
sulfate adjuvant as follows:
Type 6 (20 mcg), Type 11 (40 mcg), Type 16 (40 mcg), Type 18 (20 mcg)

Vaccine is prepared from fermentation cultures of a recombinant strain
of yeast Saccharomyces cerevisiae containing the genes for the
human papillomavirus L1 protein of each type (6, 11, 16, 18).
Contains no preservative or antibiotics.

Rx only